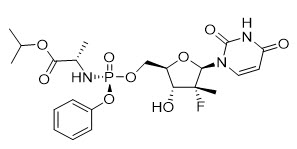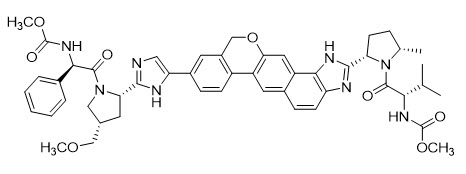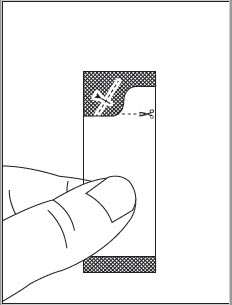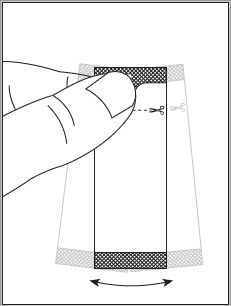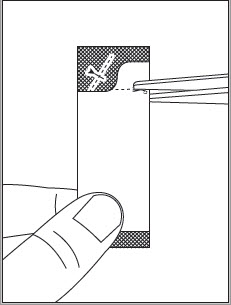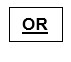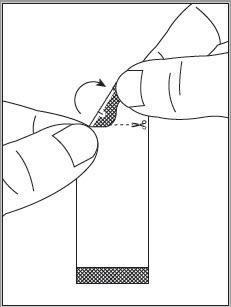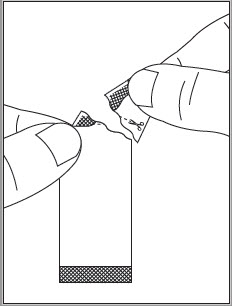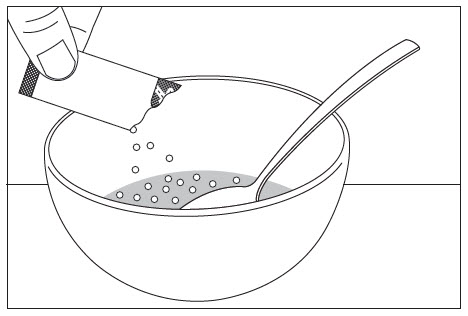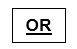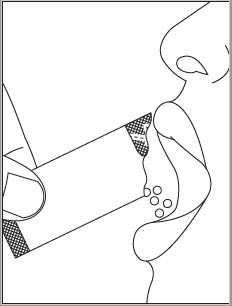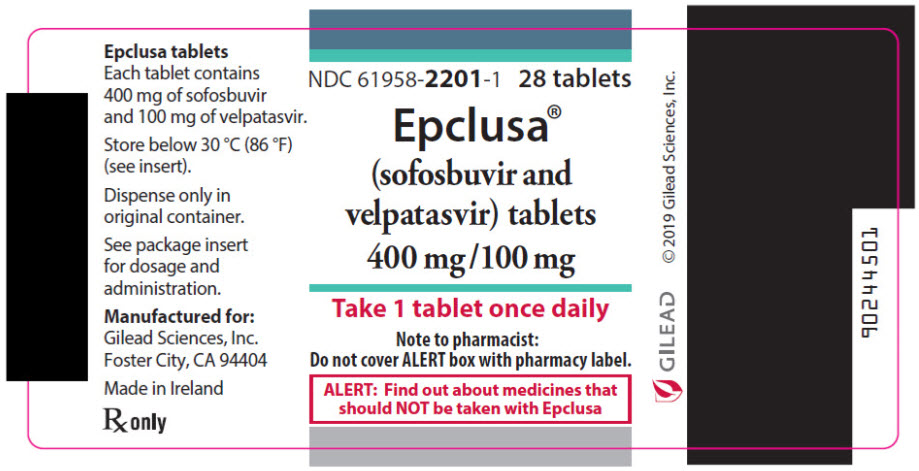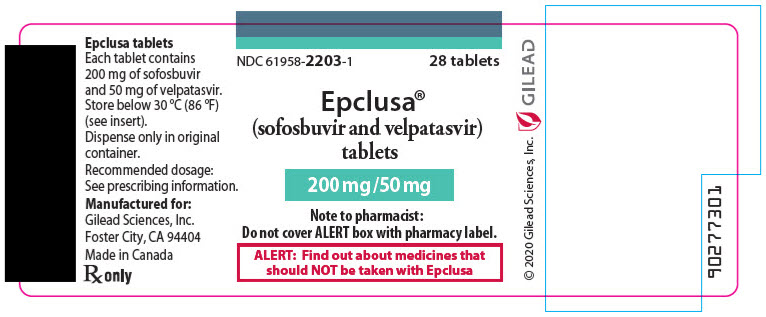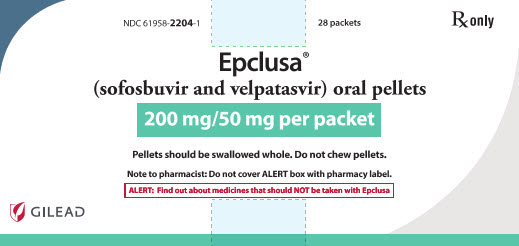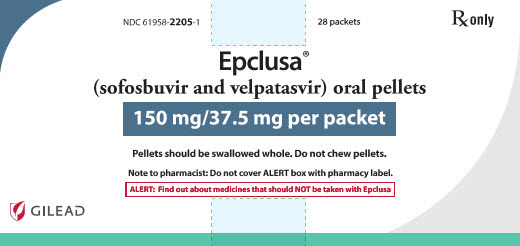 DRUG LABEL: Epclusa
NDC: 61958-2201 | Form: TABLET, FILM COATED
Manufacturer: Gilead Sciences, Inc.
Category: prescription | Type: HUMAN PRESCRIPTION DRUG LABEL
Date: 20240605

ACTIVE INGREDIENTS: VELPATASVIR 100 mg/1 1; SOFOSBUVIR 400 mg/1 1
INACTIVE INGREDIENTS: ALCOHOL; COPOVIDONE K25-31; MICROCRYSTALLINE CELLULOSE; CROSCARMELLOSE SODIUM; MAGNESIUM STEARATE; WATER; TITANIUM DIOXIDE; POLYETHYLENE GLYCOL 3350; TALC; FERRIC OXIDE RED; POLYVINYL ALCOHOL, UNSPECIFIED

HIGHLIGHTS OF PRESCRIBING INFORMATION

These highlights do not include all the information needed to use EPCLUSA safely and effectively. See full prescribing information for EPCLUSA.
EPCLUSA® (sofosbuvir and velpatasvir) tablets, for oral use
EPCLUSA® (sofosbuvir and velpatasvir) oral pellets
Initial U.S. Approval: 2016

WARNING: RISK OF HEPATITIS B VIRUS REACTIVATION IN PATIENTS COINFECTED WITH HCV AND HBV

See full prescribing information for complete boxed warning.

Hepatitis B virus (HBV) reactivation has been reported, in some cases resulting in fulminant hepatitis, hepatic failure, and death. (5.1)

RECENT MAJOR CHANGES

Indications and Usage (1) | 06/2021
Dosage and Administration
Recommended Treatment Regimen and Duration in Patients 3 Years of Age and Older (2.2) | 06/2021
Recommended Dosage in Pediatric Patients 3 Years of Age and Older (2.4) | 06/2021
Preparation and Administration of Oral Pellets (2.5) | 06/2021

1 INDICATIONS AND USAGE

EPCLUSA is a fixed-dose combination of sofosbuvir, a hepatitis C virus (HCV) nucleotide analog NS5B polymerase inhibitor, and velpatasvir, an HCV NS5A inhibitor, and is indicated for the treatment of adults and pediatric patients 3 years of age and older with chronic HCV genotype 1, 2, 3, 4, 5, or 6 infection (1):

- without cirrhosis or with compensated cirrhosis
- with decompensated cirrhosis for use in combination with ribavirin.

2 DOSAGE AND ADMINISTRATION

- Testing prior to the initiation of therapy: Test all patients for HBV infection by measuring HBsAg and anti-HBc. (2.1)
- See recommended treatment regimen and duration in patients 3 years of age and older with genotypes 1, 2, 3, 4, 5, or 6 HCV in table below: (2.2)
  Patient Population | Regimen and Duration
  Treatment-naïve and treatment-experienced [In clinical trials, regimens contained peginterferon alfa/ribavirin with or without an HCV NS3/4A protease inhibitor (boceprevir, simeprevir, or telaprevir).] , without cirrhosis and with compensated cirrhosis (Child-Pugh A) | EPCLUSA 12 weeks
  Treatment-naïve and treatment-experienced, with decompensated cirrhosis (Child-Pugh B and C) | EPCLUSA + ribavirin 12 weeks
- Recommended dosage in adults: One tablet (400 mg of sofosbuvir and 100 mg of velpatasvir) taken orally once daily with or without food. (2.3)
- Recommended dosage in pediatric patients 3 years and older: Recommended dosage is based on weight. Refer to Table 2 of the full prescribing information for specific dosing guidelines based on body weight. (2.4)
- For pediatric patients less than 6 years of age, administer EPCLUSA oral pellets with food. (2.4)
- Instructions for Use should be followed for preparation and administration of EPCLUSA oral pellets. (2.5)
- HCV/HIV-1 coinfection: For patients with HCV/HIV-1 coinfection, follow the dosage recommendations in the table above. (2.2)
- For treatment-naïve and treatment-experienced liver transplant recipients without cirrhosis or with compensated cirrhosis (Child-Pugh A), the recommended regimen is EPCLUSA once daily for 12 weeks. (2.2)
- If used in combination with ribavirin, follow the recommendations for ribavirin dosing and dosage modifications. (2.3, 2.4)
- For patients with renal impairment including end stage renal disease on dialysis, follow the dosage recommendations in the table above. (2.6)

3 DOSAGE FORMS AND STRENGTHS

- Tablets: 400 mg of sofosbuvir and 100 mg of velpatasvir; 200 mg of sofosbuvir and 50 mg of velpatasvir. (3)
- Oral Pellets: 200 mg of sofosbuvir and 50 mg of velpatasvir; 150 mg of sofosbuvir and 37.5 mg of velpatasvir. (3)

4 CONTRAINDICATIONS

EPCLUSA and ribavirin combination regimen is contraindicated in patients for whom ribavirin is contraindicated. (4)

5 WARNINGS AND PRECAUTIONS

- Risk of Hepatitis B Virus Reactivation: Test all patients for evidence of current or prior HBV infection before initiation of HCV treatment. Monitor HCV/HBV coinfected patients for HBV reactivation and hepatitis flare during HCV treatment and post-treatment follow-up. Initiate appropriate patient management for HBV infection as clinically indicated. (5.1)
- Bradycardia with amiodarone coadministration: Serious symptomatic bradycardia may occur in patients taking amiodarone, particularly in patients also receiving beta blockers, or those with underlying cardiac comorbidities and/or advanced liver disease. Coadministration of amiodarone with EPCLUSA is not recommended. In patients without alternative viable treatment options, cardiac monitoring is recommended. (5.2, 7.3)

6 ADVERSE REACTIONS

- The most common adverse reactions (incidence greater than or equal to 10%, all grades) observed in adults and pediatric subjects 6 years of age and older with treatment with EPCLUSA for 12 weeks are headache and fatigue. (6.1)
- The most common adverse reactions (incidence greater than or equal to 10%, grade 1 or 2) observed in pediatric subjects less than 6 years of age are vomiting and product use issue (spitting up the drug). (6.1)
- The most common adverse reactions (incidence greater than or equal to 10%, all grades) observed with treatment with EPCLUSA and ribavirin for 12 weeks in adult patients with decompensated cirrhosis are fatigue, anemia, nausea, headache, insomnia, and diarrhea. (6.1)

To report SUSPECTED ADVERSE REACTIONS, contact Gilead Sciences, Inc. at 1-800-GILEAD-5 or FDA at 1-800-FDA-1088 or www.fda.gov/medwatch.

7 DRUG INTERACTIONS

- P-gp inducers and/or moderate to strong CYP inducers (e.g., rifampin, St. John's wort, carbamazepine): May decrease concentrations of sofosbuvir and/or velpatasvir. Use of EPCLUSA with P-gp inducers and/or moderate to strong CYP inducers is not recommended. (5.3, 7)
- Consult the full prescribing information prior to use for potential drug interactions. (5.2, 5.3, 7)
- Clearance of HCV infection with direct acting antivirals may lead to changes in hepatic function, which may impact safe and effective use of concomitant medications. Frequent monitoring of relevant laboratory parameters (INR or blood glucose) and dose adjustments of certain concomitant medications may be necessary. (7.3)

FULL PRESCRIBING INFORMATION

WARNING: RISK OF HEPATITIS B VIRUS REACTIVATION IN PATIENTS COINFECTED WITH HCV AND HBV

Test all patients for evidence of current or prior hepatitis B virus (HBV) infection before initiating treatment with EPCLUSA. HBV reactivation has been reported in HCV/HBV coinfected patients who were undergoing or had completed treatment with HCV direct acting antivirals and were not receiving HBV antiviral therapy. Some cases have resulted in fulminant hepatitis, hepatic failure, and death. Monitor HCV/HBV coinfected patients for hepatitis flare or HBV reactivation during HCV treatment and post-treatment follow-up. Initiate appropriate patient management for HBV infection as clinically indicated [see Warnings and Precautions (5.1)].

1 INDICATIONS AND USAGE

EPCLUSA is indicated for the treatment of adults and pediatric patients 3 years of age and older with chronic hepatitis C virus (HCV) genotype 1, 2, 3, 4, 5, or 6 infection [see Dosage and Administration (2.2, 2.3, 2.4) and Clinical Studies (14)]:

- without cirrhosis or with compensated cirrhosis
- with decompensated cirrhosis for use in combination with ribavirin.

2 DOSAGE AND ADMINISTRATION

2.1 Testing Prior to the Initiation of Therapy

Test all patients for evidence of current or prior HBV infection by measuring hepatitis B surface antigen (HBsAg) and hepatitis B core antibody (anti-HBc) before initiating HCV treatment with EPCLUSA [see Warnings and Precautions (5.1)].

2.2 Recommended Treatment Regimen and Duration in Patients 3 Years of Age and Older

Table 1 shows the recommended treatment regimen and duration based on patient population.

For patients with HCV/HIV-1 coinfection follow the dosage recommendations in Table 1. For treatment-naïve and treatment-experienced liver transplant recipients without cirrhosis or with compensated cirrhosis (Child-Pugh A), the recommended regimen is EPCLUSA once daily for 12 weeks [see Clinical Studies (14.3 and 14.5)]. Refer to Drug Interactions (7) for dosage recommendations for concomitant drugs.

Table 1 Recommended Treatment Regimen and Duration in Patients 3 Years of Age and Older with Genotype 1, 2, 3, 4, 5, or 6 HCV
Patient Population | Treatment Regimen and Duration
Treatment-naïve and treatment-experienced [In clinical trials in adults, regimens contained peginterferon alfa/ribavirin with or without an HCV NS3/4A protease inhibitor (boceprevir, simeprevir, or telaprevir).] , without cirrhosis and with compensated cirrhosis (Child-Pugh A) | EPCLUSA 12 weeks
Treatment-naïve and treatment-experienced, with decompensated cirrhosis (Child-Pugh B or C) | EPCLUSA + ribavirin [See Dosage and Administration 2.3 and 2.4 for ribavirin dosage recommendations.] 12 weeks

2.3 Recommended Dosage in Adults

The recommended dosage of EPCLUSA in adults is one tablet (400 mg sofosbuvir and 100 mg velpatasvir) taken orally once daily with or without food [see Clinical Pharmacology (12.3)].

When administered with EPCLUSA, the recommended dosage of ribavirin is based on weight (administered with food): 1,000 mg per day for patients less than 75 kg and 1,200 mg for those weighing at least 75 kg, divided and administered twice daily. The starting dosage and on-treatment dosage of ribavirin can be decreased based on hemoglobin and creatinine clearance. For ribavirin dosage modifications refer to the ribavirin prescribing information [see Use in Specific Populations (8.6) and Clinical Studies (14.4)].

2.4 Recommended Dosage in Pediatric Patients 3 Years of Age and Older

The recommended dosage of EPCLUSA in pediatric patients 3 years of age and older is based on weight and provided in Table 2. Table 3 provides the weight-based dosage of ribavirin when used in combination with EPCLUSA for pediatric patients. Take EPCLUSA oral pellets or tablets once daily with or without food. In pediatric patients less than 6 years of age, administer the oral pellets with food to increase tolerability related to palatability [see Use in Specific Populations (8.4), Clinical Pharmacology (12.3), and Clinical Studies (14.8)].

Table 2 Dosing for Pediatric Patients 3 Years and Older with Genotype 1, 2, 3, 4, 5, or 6 HCV Using EPCLUSA Oral Pellets or Tablets
Body Weight (kg) | EPCLUSA Daily Dose | Dosing of EPCLUSA Oral Pellets | Dosing of EPCLUSA Tablet
less than 17 | 150 mg/37.5 mg per day | one 150 mg/37.5 mg packet of pellets once daily | N/A
17 to less than 30 | 200 mg/50 mg per day | one 200 mg/50 mg packet of pellets once daily | one 200 mg/50 mg tablet once daily
at least 30 | 400 mg/100 mg per day | two 200 mg/50 mg packets of pellets once daily | one 400 mg/100 mg tablet once daily [Two 200 mg/50 mg tablets once daily can be used for patients who cannot swallow the 400 mg/100 mg tablet.]

Table 3 Recommended Dosing for Ribavirin in Combination Therapy with EPCLUSA for Pediatric Patients 3 Years and Older
Body Weight (kg) | Oral Ribavirin Daily Dosage [The daily dosage of ribavirin is weight-based and is administered orally in two divided doses with food.]
less than 47 | 15 mg per kg per day (divided dose AM and PM)
47–49 | 600 mg per day (1 × 200 mg AM, 2 × 200 mg PM)
50–65 | 800 mg per day (2 × 200 mg AM, 2 × 200 mg PM)
66–80 | 1,000 mg per day (2 × 200 mg AM, 3 × 200 mg PM)
greater than 80 | 1,200 mg per day (3 × 200 mg AM, 3 × 200 mg PM)

2.5 Preparation and Administration of Oral Pellets

See the EPCLUSA oral pellets full Instructions for Use for details on the preparation and administration of EPCLUSA oral pellets.

Do not chew EPCLUSA oral pellets to avoid a bitter aftertaste. EPCLUSA oral pellets can be taken directly in the mouth or with food (See Instructions for Use). In pediatric patients less than 6 years of age, administer the oral pellets with food to increase tolerability related to palatability. Sprinkle the oral pellets on one or more spoonfuls of non-acidic soft food at or below room temperature. Examples of non-acidic foods include pudding, chocolate syrup, and ice cream. Take EPCLUSA oral pellets within 15 minutes of gently mixing with food and swallow the entire contents without chewing.

2.6 Renal Impairment

No dosage adjustment of EPCLUSA is recommended in patients with any degree of renal impairment, including patients requiring dialysis. Administer EPCLUSA with or without ribavirin according to the recommendations in Table 1 [see Adverse Reactions (6.1), Use in Specific Populations (8.6), and Clinical Studies (14.6)]. Refer to ribavirin tablet prescribing information for ribavirin dosage modification for patients with CrCl less than or equal to 50 mL per minute.

3 DOSAGE FORMS AND STRENGTHS

EPCLUSA is available as tablets or pellets for oral use. Each dosage form is available in two dose strengths:

- 400 mg/100 mg Tablets: pink, diamond-shaped, film-coated tablet debossed with "GSI" on one side and "7916" on the other side. Each tablet contains 400 mg of sofosbuvir and 100 mg of velpatasvir.
- 200 mg/50 mg Tablets: pink, oval-shaped, film-coated tablet debossed with "GSI" on one side and "S/V" on the other side. Each tablet contains 200 mg of sofosbuvir and 50 mg of velpatasvir.
- 200 mg/50 mg Oral Pellets: white to off-white, film-coated pellets in unit-dose packets. Each packet contains 200 mg of sofosbuvir and 50 mg of velpatasvir.
- 150 mg/37.5 mg Oral Pellets: white to off-white, film-coated pellets in unit-dose packets. Each packet contains 150 mg of sofosbuvir and 37.5 mg of velpatasvir.

4 CONTRAINDICATIONS

EPCLUSA and ribavirin combination regimen is contraindicated in patients for whom ribavirin is contraindicated. Refer to the ribavirin prescribing information for a list of contraindications for ribavirin [see Dosage and Administration (2.2, 2.3, 2.4)].

5 WARNINGS AND PRECAUTIONS

5.1 Risk of Hepatitis B Virus Reactivation in Patients Coinfected with HCV and HBV

Hepatitis B virus (HBV) reactivation has been reported in HCV/HBV coinfected patients who were undergoing or had completed treatment with HCV direct acting antivirals, and who were not receiving HBV antiviral therapy. Some cases have resulted in fulminant hepatitis, hepatic failure, and death. Cases have been reported in patients who are HBsAg positive and also in patients with serologic evidence of resolved HBV infection (i.e., HBsAg negative and anti-HBc positive). HBV reactivation has also been reported in patients receiving certain immunosuppressants or chemotherapeutic agents; the risk of HBV reactivation associated with treatment with HCV direct-acting antivirals may be increased in these patients.

HBV reactivation is characterized as an abrupt increase in HBV replication manifesting as a rapid increase in serum HBV DNA level. In patients with resolved HBV infection, reappearance of HBsAg can occur. Reactivation of HBV replication may be accompanied by hepatitis, i.e., increases in aminotransferase levels and, in severe cases, increases in bilirubin levels, liver failure, and death can occur.

Test all patients for evidence of current or prior HBV infection by measuring HBsAg and anti-HBc before initiating HCV treatment with EPCLUSA. In patients with serologic evidence of HBV infection, monitor for clinical and laboratory signs of hepatitis flare or HBV reactivation during HCV treatment with EPCLUSA and during post-treatment follow-up. Initiate appropriate patient management for HBV infection as clinically indicated.

5.2 Serious Symptomatic Bradycardia When Coadministered with Amiodarone

Postmarketing cases of symptomatic bradycardia and cases requiring pacemaker intervention have been reported when amiodarone is coadministered with a sofosbuvir-containing regimen. A fatal cardiac arrest was reported in a patient taking amiodarone who was coadministered a sofosbuvir-containing regimen (HARVONI® [ledipasvir/sofosbuvir]). Bradycardia has generally occurred within hours to days, but cases have been observed up to 2 weeks after initiating HCV treatment. Patients also taking beta blockers, or those with underlying cardiac comorbidities and/or advanced liver disease may be at increased risk for symptomatic bradycardia with coadministration of amiodarone. Bradycardia generally resolved after discontinuation of HCV treatment. The mechanism for this effect is unknown.

Coadministration of amiodarone with EPCLUSA is not recommended. For patients taking amiodarone who have no other alternative viable treatment options and who will be coadministered EPCLUSA:

- Counsel patients about the risk of symptomatic bradycardia.
- Cardiac monitoring in an in-patient setting for the first 48 hours of coadministration is recommended, after which outpatient or self-monitoring of the heart rate should occur on a daily basis through at least the first 2 weeks of treatment.

Patients who are taking EPCLUSA who need to start amiodarone therapy due to no other alternative viable treatment options should undergo similar cardiac monitoring as outlined above.

Due to amiodarone's long half-life, patients discontinuing amiodarone just prior to starting EPCLUSA should also undergo similar cardiac monitoring as outlined above.

Patients who develop signs or symptoms of bradycardia should seek medical evaluation immediately. Symptoms may include near-fainting or fainting, dizziness or lightheadedness, malaise, weakness, excessive tiredness, shortness of breath, chest pains, confusion, or memory problems [see Adverse Reactions (6.2) and Drug Interactions (7.3)].

5.3 Risk of Reduced Therapeutic Effect Due to Concomitant Use of EPCLUSA with Inducers of P-gp and/or Moderate to Strong Inducers of CYP

Drugs that are inducers of P-gp and/or moderate to strong inducers of CYP2B6, CYP2C8, or CYP3A4 (e.g., rifampin, St. John's wort, carbamazepine) may significantly decrease plasma concentrations of sofosbuvir and/or velpatasvir, leading to potentially reduced therapeutic effect of EPCLUSA. The use of these agents with EPCLUSA is not recommended [see Drug Interactions (7.3)].

5.4 Risks Associated with Ribavirin and EPCLUSA Combination Treatment

If EPCLUSA is administered with ribavirin, the warnings and precautions for ribavirin apply to this combination regimen. Refer to the ribavirin prescribing information for a full list of the warnings and precautions for ribavirin [see Dosage and Administration (2.2)].

6 ADVERSE REACTIONS

The following serious adverse reactions are described below and elsewhere in labeling:

- Serious Symptomatic Bradycardia When Coadministered with Amiodarone [see Warnings and Precautions (5.2)].

6.1 Clinical Trials Experience

Because clinical trials are conducted under widely varying conditions, adverse reaction rates observed in the clinical trials of a drug cannot be directly compared to rates in the clinical trials of another drug and may not reflect the rates observed in practice.

If EPCLUSA is administered with ribavirin, refer to the prescribing information for ribavirin for a description of ribavirin-associated adverse reactions.

Clinical Trials in Adult Subjects

Adverse Reactions in Subjects without Cirrhosis or with Compensated Cirrhosis

The adverse reactions data for EPCLUSA in patients without cirrhosis or with compensated cirrhosis were derived from three Phase 3 clinical trials (ASTRAL-1, ASTRAL-2, and ASTRAL-3) which evaluated a total of 1035 subjects infected with genotype 1, 2, 3, 4, 5, or 6 HCV, without cirrhosis or with compensated cirrhosis, who received EPCLUSA for 12 weeks. EPCLUSA was studied in placebo- and active-controlled trials [see Clinical Studies (14.2)].

The proportion of subjects who permanently discontinued treatment due to adverse events was 0.2% for subjects who received EPCLUSA for 12 weeks.

The most common adverse reactions (adverse events assessed as causally related by the investigator and at least 10%) were headache and fatigue in subjects treated with EPCLUSA for 12 weeks.

Adverse reactions, all grades, observed in greater than or equal to 5% of subjects receiving 12 weeks of treatment with EPCLUSA in ASTRAL-1 include headache (22%), fatigue (15%), nausea (9%), asthenia (5%), and insomnia (5%). Of subjects receiving EPCLUSA who experienced these adverse reactions, 79% had an adverse reaction of mild severity (Grade 1). With the exception of asthenia, each of these adverse reactions occurred at a similar frequency or more frequently in subjects treated with placebo compared to subjects treated with EPCLUSA (asthenia: 3% versus 5% for the placebo and EPCLUSA groups, respectively).

The adverse reactions observed in subjects treated with EPCLUSA in ASTRAL-2 and ASTRAL-3 were consistent with those observed in ASTRAL-1. Irritability was also observed in greater than or equal to 5% of subjects treated with EPCLUSA in ASTRAL-3.

Adverse Reactions in Subjects Coinfected with HCV and HIV-1

The safety assessment of EPCLUSA in subjects with HCV/HIV-1 coinfection was based on an open-label clinical trial (ASTRAL-5) in 106 subjects who were on stable antiretroviral therapy [see Clinical Studies (14.3)]. The safety profile in HCV/HIV-1 coinfected subjects was similar to that observed in HCV mono-infected subjects. The most common adverse reactions occurring in at least 10% of subjects were fatigue (22%) and headache (10%).

Adverse Reactions in Subjects with Decompensated Cirrhosis

The safety assessment of EPCLUSA in subjects infected with genotype 1, 2, 3, 4, or 6 HCV with decompensated cirrhosis was based on one Phase 3 trial (ASTRAL-4) including 87 subjects who received EPCLUSA with ribavirin for 12 weeks. All 87 subjects had Child-Pugh B cirrhosis at screening. On the first day of treatment with EPCLUSA with ribavirin, 6 subjects and 4 subjects were assessed to have Child-Pugh A and Child-Pugh C cirrhosis, respectively [see Clinical Studies (14.4)].

The most common adverse reactions (adverse events assessed as causally related by the investigator, all grades with frequency of 10% or greater) in the 87 subjects who received EPCLUSA with ribavirin for 12 weeks were fatigue (32%), anemia (26%), nausea (15%), headache (11%), insomnia (11%), and diarrhea (10%). Of subjects who experienced these adverse reactions, 98% had adverse reactions of mild to moderate severity.

A total of 4 (5%) subjects permanently discontinued EPCLUSA with ribavirin due to an adverse event; there was no adverse event leading to discontinuation that occurred in more than 1 subject.

Decreases in hemoglobin to less than 10 g/dL and 8.5 g/dL during treatment were observed in 23% and 7% of subjects treated with EPCLUSA with ribavirin for 12 weeks, respectively. Ribavirin was permanently discontinued in 17% of subjects treated with EPCLUSA with ribavirin for 12 weeks, due to adverse reactions.

Less Common Adverse Reactions Reported in Clinical Trials

The following adverse reactions occurred in less than 5% of subjects without cirrhosis or with compensated cirrhosis treated with EPCLUSA for 12 weeks and are included because of a potential causal relationship.

Rash: In the ASTRAL-1 study, rash occurred in 2% of subjects treated with EPCLUSA and in 1% of subjects treated with placebo. No serious adverse reactions of rash occurred, and all rashes were mild or moderate in severity.

Depression: In the ASTRAL-1 study, depressed mood occurred in 1% of subjects treated with EPCLUSA and was not reported by any subject taking placebo. No serious adverse reactions of depressed mood occurred, and all events were mild or moderate in severity.

The following adverse reactions occurred in less than 10% of subjects with decompensated cirrhosis (ASTRAL-4) treated with EPCLUSA with ribavirin for 12 weeks and are included because of a potential causal relationship.

Rash: Rash occurred in 5% of subjects treated with EPCLUSA with ribavirin. No serious adverse reactions of rash occurred, and all rashes were mild or moderate in severity.

Laboratory Abnormalities

Lipase Elevations: In ASTRAL-1, isolated, asymptomatic lipase elevations of greater than 3×ULN were observed in 3% and 1% of subjects treated with EPCLUSA and placebo for 12 weeks, respectively; and in 6% and 3% of subjects treated with EPCLUSA in ASTRAL-2 and ASTRAL-3, respectively.

In the Phase 3 trial of subjects with decompensated cirrhosis (ASTRAL-4), lipase was assessed when amylase values were greater than or equal to 1.5×ULN. Isolated, asymptomatic lipase elevations of greater than 3×ULN were observed in 2% of subjects treated with EPCLUSA with ribavirin for 12 weeks.

Creatine Kinase: In ASTRAL-1, isolated, asymptomatic creatine kinase elevations greater than or equal to 10×ULN were reported in 1% and 0% of subjects treated with EPCLUSA and placebo for 12 weeks, respectively; and in 2% and 1% of subjects treated with EPCLUSA in ASTRAL-2 and ASTRAL-3, respectively.

In the Phase 3 trial with decompensated cirrhosis (ASTRAL-4), isolated, asymptomatic creatine kinase elevations greater than or equal to 10×ULN were reported in 1% of subjects treated with EPCLUSA with ribavirin for 12 weeks.

Indirect Bilirubin: Increases in indirect bilirubin up to 3 mg/dL above baseline were noted among HIV-1/HCV coinfected subjects treated with EPCLUSA and an atazanavir/ritonavir-based antiretroviral regimen. The elevated indirect bilirubin values were not associated with clinical adverse events, and all subjects completed 12 weeks of EPCLUSA without dose adjustment or treatment interruption of either EPCLUSA or HIV antiretroviral agents.

Adverse Reactions in Adult Liver Transplant Recipients

The safety assessment of EPCLUSA in liver transplant recipients was based on an open-label clinical trial (Trial 2104) in 79 adults without cirrhosis or with compensated cirrhosis who received EPCLUSA for 12 weeks [see Clinical Studies (14.5)]. One subject discontinued treatment due to an adverse event on Day 7. The adverse reactions observed were consistent with the known safety profile of EPCLUSA. Adverse reactions occurring in at least 5% of subjects were headache (18%), fatigue (15%), nausea (8%), diarrhea (6%), and asthenia (5%).

Adverse Reactions in Adults with Severe Renal Impairment Requiring Dialysis

In an open-label trial (Trial 4062), in which a total of 59 adults with HCV with compensated liver disease (with or without cirrhosis) and ESRD requiring dialysis received EPCLUSA for 12 weeks, the most common adverse reaction was nausea (7%) [see Clinical Studies (14.6)].

Adverse Reactions in People Who Inject Drugs (PWID), Including Those on Medication-Assisted Treatment (MAT) for Opioid Use Disorder

The safety of EPCLUSA in PWID is based on an open-label Phase 2 trial (SIMPLIFY) that enrolled 103 adult subjects with chronic HCV genotype 1, 2, 3, and 4 infection. Subjects who self-reported injection drug use within the 6 months prior to starting treatment were eligible and were treated with EPCLUSA for 12 weeks. The trial included a subset of 58 subjects on MAT for opioid use disorder.

The adverse reactions observed from SIMPLIFY both overall and in subjects on MAT were consistent with the known safety profile of EPCLUSA. The most common adverse reactions overall were fatigue (18%), nausea (13%), and headache (11%) [see Use in Specific Populations (8.8) and Clinical Studies (14.7)]. Adverse reactions leading to permanent discontinuation of treatment were not observed in any subjects.

Adverse Reactions in Pediatric Subjects 3 Years of Age and Older

The safety assessment of EPCLUSA in pediatric subjects 3 years of age and older is based on data from a Phase 2, open-label clinical trial (Study 1143) that enrolled 216 subjects who were treated with EPCLUSA for 12 weeks [see Clinical Studies (14.8)]. The adverse reactions observed in pediatric subjects 6 years of age and older were consistent with those observed in clinical trials of EPCLUSA in adults.

Among the 41 pediatric subjects less than 6 years of age, gastrointestinal adverse reactions were reported more commonly compared to subjects 6 years of age and older. Vomiting and product use issue (spitting up the drug) were reported in 15% and 10% of subjects, respectively; these adverse reactions were mild (Grade 1 or 2) and led to treatment discontinuation in 5 (12%) subjects [see Use in Specific Populations (8.4) and Clinical Studies (14.8)].

6.2 Postmarketing Experience

The following adverse reactions have been identified during post approval use of sofosbuvir. Because postmarketing reactions are reported voluntarily from a population of uncertain size, it is not always possible to reliably estimate their frequency or establish a causal relationship to drug exposure.

Cardiac Disorders

Serious symptomatic bradycardia has been reported in patients taking amiodarone who initiate treatment with a sofosbuvir-containing regimen [see Warnings and Precautions (5.2) and Drug Interactions (7.3)].

Skin and Subcutaneous Tissue Disorders

Skin rashes, sometimes with blisters or angioedema-like swelling

Angioedema

7 DRUG INTERACTIONS

7.1 Potential for Other Drugs to Affect EPCLUSA

Sofosbuvir and velpatasvir are substrates of drug transporters P-gp and BCRP while GS-331007 (the predominant circulating metabolite of sofosbuvir) is not. In vitro, slow metabolic turnover of velpatasvir by CYP2B6, CYP2C8, and CYP3A4 was observed.

Drugs that are inducers of P-gp and/or moderate to strong inducers of CYP2B6, CYP2C8, or CYP3A4 (e.g., rifampin, St. John's wort, carbamazepine) may decrease plasma concentrations of sofosbuvir and/or velpatasvir, leading to reduced therapeutic effect of EPCLUSA. The use of these agents with EPCLUSA is not recommended [see Warnings and Precautions (5.3) and Clinical Pharmacology (12.3)]. EPCLUSA may be coadministered with P-gp, BCRP, and CYP inhibitors.

7.2 Potential for EPCLUSA to Affect Other Drugs

Velpatasvir is an inhibitor of drug transporters P-gp, breast cancer resistance protein (BCRP), OATP1B1, OATP1B3, and OATP2B1. Coadministration of EPCLUSA with drugs that are substrates of these transporters may increase the exposure of such drugs.

7.3 Established and Potentially Significant Drug Interactions

Clearance of HCV infection with direct acting antivirals may lead to changes in hepatic function, which may impact the safe and effective use of concomitant medications. For example, altered blood glucose control resulting in serious symptomatic hypoglycemia has been reported in diabetic patients in postmarketing case reports and published epidemiological studies. Management of hypoglycemia in these cases required either discontinuation or dose modification of concomitant medications used for diabetes treatment.

Frequent monitoring of relevant laboratory parameters (e.g., International Normalized Ratio [INR] in patients taking warfarin, blood glucose levels in diabetic patients) or drug concentrations of concomitant medications such as cytochrome P450 substrates with a narrow therapeutic index (e.g., certain immunosuppressants) is recommended to ensure safe and effective use. Dose adjustments of concomitant medications may be necessary.

Table 4 provides a listing of established or potentially clinically significant drug interactions. The drug interactions described are based on studies conducted with either EPCLUSA, the components of EPCLUSA (sofosbuvir and velpatasvir) as individual agents, or are predicted drug interactions that may occur with EPCLUSA [see Warnings and Precautions (5.2, 5.3) and Clinical Pharmacology (12.3)].

Table 4 Potentially Significant Drug Interactions: Alteration in Dose or Regimen May Be Recommended Based on Drug Interaction Studies or Predicted Interaction [This table is not all inclusive.]
Concomitant Drug Class: Drug Name | Effect on Concentration [↓ = decrease, ↑ = increase.] | Clinical Effect/Recommendation
Acid Reducing Agents: | ↓ velpatasvir | Velpatasvir solubility decreases as pH increases. Drugs that increase gastric pH are expected to decrease concentration of velpatasvir.
Antacids (e.g., aluminum and magnesium hydroxide) | ↓ velpatasvir | Separate antacid and EPCLUSA administration by 4 hours.
H2-receptor antagonists [These interactions have been studied in healthy adults.] (e.g., famotidine) | ↓ velpatasvir | H2-receptor antagonists may be administered simultaneously with or 12 hours apart from EPCLUSA at a dose that does not exceed doses comparable to famotidine 40 mg twice daily.
Proton-pump inhibitors (e.g., omeprazole) | ↓ velpatasvir | Coadministration of omeprazole or other proton-pump inhibitors is not recommended. If it is considered medically necessary to coadminister, EPCLUSA should be administered with food and taken 4 hours before omeprazole 20 mg. Use with other proton-pump inhibitors has not been studied.
Antiarrhythmics: amiodarone | Effect on amiodarone, sofosbuvir, and velpatasvir concentrations unknown | Coadministration of amiodarone with a sofosbuvir-containing regimen may result in serious symptomatic bradycardia. The mechanism of this effect is unknown. Coadministration of amiodarone with EPCLUSA is not recommended; if coadministration is required, cardiac monitoring is recommended [see Warnings and Precautions (5.2) and Adverse Reactions (6.2)].
digoxin | ↑ digoxin | Therapeutic concentration monitoring of digoxin is recommended when coadministered with EPCLUSA. Refer to digoxin prescribing information for monitoring and dose modification recommendations for concentration increases of less than 50%.
Anticancers: topotecan | ↑ topotecan | Coadministration is not recommended.
Anticonvulsants: carbamazepine phenytoin phenobarbital | ↓ sofosbuvir ↓ velpatasvir | Coadministration is not recommended.
Antimycobacterials: rifabutin rifampin rifapentine | ↓ sofosbuvir ↓ velpatasvir | Coadministration is not recommended.
HIV Antiretrovirals: efavirenz | ↓ velpatasvir | Coadministration of EPCLUSA with efavirenz-containing regimens is not recommended.
Regimens containing tenofovir DF | ↑ tenofovir | Monitor for tenofovir-associated adverse reactions in patients receiving EPCLUSA concomitantly with a regimen containing tenofovir DF. Refer to the prescribing information of the tenofovir DF-containing product for recommendations on renal monitoring.
tipranavir/ritonavir | ↓ sofosbuvir ↓ velpatasvir | Coadministration is not recommended.
Herbal Supplements: St. John's wort (Hypericum perforatum) | ↓ sofosbuvir ↓ velpatasvir | Coadministration is not recommended.
HMG-CoA Reductase Inhibitors: rosuvastatin | ↑ rosuvastatin | Coadministration of EPCLUSA with rosuvastatin may significantly increase the concentration of rosuvastatin, which is associated with increased risk of myopathy, including rhabdomyolysis. Rosuvastatin may be administered with EPCLUSA at a dose that does not exceed 10 mg.
atorvastatin | ↑ atorvastatin | Coadministration of EPCLUSA with atorvastatin may be associated with increased risk of myopathy, including rhabdomyolysis. Monitor closely for HMG-CoA reductase inhibitor-associated adverse reactions, such as myopathy and rhabdomyolysis.
DF = disoproxil fumarate.

7.4 Drugs without Clinically Significant Interactions with EPCLUSA

Based on drug interaction studies conducted with the components of EPCLUSA (sofosbuvir or velpatasvir) or EPCLUSA, no clinically significant drug interactions have been observed or are expected with the following drugs [see Clinical Pharmacology (12.3)]:

- EPCLUSA: atazanavir/ritonavir, buprenorphine/naloxone, cyclosporine, darunavir/ritonavir, dolutegravir, elvitegravir/cobicistat/emtricitabine/tenofovir alafenamide, emtricitabine, methadone, naltrexone, raltegravir, or rilpivirine.
- Sofosbuvir: ethinyl estradiol/norgestimate, or tacrolimus.
- Velpatasvir: ethinyl estradiol/norgestimate, ketoconazole, or pravastatin.

See Table 4 for use of EPCLUSA with certain HIV antiretroviral regimens [see Drug Interactions (7.3)].

8 USE IN SPECIFIC POPULATIONS

8.1 Pregnancy

Risk Summary

If EPCLUSA is administered with ribavirin, the combination regimen is contraindicated in pregnant women and in men whose female partners are pregnant. Refer to the ribavirin prescribing information for more information on ribavirin-associated risks of use during pregnancy.

No adequate human data are available to establish whether or not EPCLUSA poses a risk to pregnancy outcomes. In animal reproduction studies, no evidence of adverse developmental outcomes was observed with the components of EPCLUSA (sofosbuvir or velpatasvir) at exposures greater than those in humans at the recommended human dose (RHD) [see Data]. During organogenesis in the mouse, rat, and rabbit, systemic exposures (AUC) to velpatasvir were approximately 31 (mice), 6 (rats), and 0.4 (rabbits) times the exposure in humans at the RHD, while exposures to the predominant circulating metabolite of sofosbuvir (GS-331007) were approximately 4 (rats) and 10 (rabbits) times the exposure in humans at the RHD. In rat pre/postnatal development studies, maternal systemic exposures (AUC) to velpatasvir and GS-331007 were approximately 5 times the exposures of each component in humans at the RHD.

The background risk of major birth defects and miscarriage for the indicated population is unknown. In the U.S. general population, the estimated background risk of major birth defects and miscarriage in clinically recognized pregnancies is 2–4% and 15–20%, respectively.

Data

Sofosbuvir: Sofosbuvir was administered orally to pregnant rats (up to 500 mg/kg/day) and rabbits (up to 300 mg/kg/day) on gestation days 6 to 18 and 6 to 19, respectively, and also to rats (oral doses up to 500 mg/kg/day) on gestation day 6 to lactation/post-partum day 20. No significant effects on embryo-fetal (rats and rabbits) or pre/postnatal (rats) development were observed at the highest doses tested. The systemic exposures (AUC) of the predominant circulating metabolite of sofosbuvir (GS-331007) during gestation were approximately 4 (rats) and 10 (rabbits) times the exposure in humans at the RHD.

Velpatasvir: Velpatasvir was administered orally to pregnant mice (up to 1000 mg/kg/day), rats (up to 200 mg/kg/day), and rabbits (up to 300 mg/kg/day) on gestation days 6 to 15, 6 to 17, and 7 to 20, respectively, and also to rats (oral doses up to 200 mg/kg) on gestation day 6 to lactation/post-partum day 20. No significant effects on embryo-fetal (mice, rats, and rabbits) or pre/postnatal (rats) development were observed at the highest doses tested. The systemic exposures (AUC) of velpatasvir during gestation were approximately 31 (mice), 6 (rats), and 0.4 (rabbits) times the exposure in humans at the RHD.

8.2 Lactation

Risk Summary

It is not known whether the components of EPCLUSA and its metabolites are present in human breast milk, affect human milk production, or have effects on the breastfed infant. The predominant circulating metabolite of sofosbuvir (GS-331007) was the primary component observed in the milk of lactating rats administered sofosbuvir, without effect on nursing pups. When administered to lactating rats, velpatasvir was detected in the milk of lactating rats and in the plasma of nursing pups without effects on the nursing pups [see Data].

The development and health benefits of breastfeeding should be considered along with the mother's clinical need for EPCLUSA and any potential adverse effects on the breastfed child from EPCLUSA or from the underlying maternal condition.

If EPCLUSA is administered with ribavirin, the nursing mother's information for ribavirin also applies to this combination regimen. Refer to the ribavirin prescribing information for more information on use during lactation.

Data

Sofosbuvir: No effects of sofosbuvir on growth and postnatal development were observed in nursing pups at the highest dose tested in rats. Maternal systemic exposure (AUC) to the predominant circulating metabolite of sofosbuvir (GS-331007) was approximately 5 times the exposure in humans at the RHD, with exposure of approximately 2% that of maternal exposure observed in nursing pups on lactation day 10. In a lactation study, sofosbuvir metabolites (primarily GS-331007) were excreted into the milk of lactating rats following administration of a single oral dose of sofosbuvir (20 mg/kg) on lactation day 2, with milk concentrations of approximately 10% that of maternal plasma concentrations observed 1-hour post-dose.

Velpatasvir: No effects of velpatasvir on growth and postnatal development were observed in nursing pups at the highest dose tested in rats. Maternal systemic exposure (AUC) to velpatasvir was approximately 5 times the exposure in humans at the RHD. Velpatasvir was present in the milk (approximately 173% that of maternal plasma concentrations) of lactating rats following a single oral dose of velpatasvir (30 mg/kg), and systemic exposure (AUC) in nursing pups was approximately 4% that of maternal exposure on lactation day 10.

8.3 Females and Males of Reproductive Potential

If EPCLUSA is administered with ribavirin, the information for ribavirin with regard to pregnancy testing, contraception, and infertility also applies to this combination regimen. Refer to ribavirin prescribing information for additional information.

8.4 Pediatric Use

The pharmacokinetics, safety, and effectiveness of EPCLUSA for treatment of HCV genotype 1, 2, 3, 4, or 6 infection in treatment-naïve and treatment-experienced pediatric patients 3 years of age and older without cirrhosis or with compensated cirrhosis have been established in an open-label, multicenter clinical trial (Study 1143, N=216; 190 treatment-naïve, 26 treatment-experienced). No clinically meaningful differences in pharmacokinetics were observed in comparison to those observed in adults.

The safety and effectiveness in pediatric subjects were comparable to those observed in adults. However, among the 41 pediatric subjects less than 6 years of age, vomiting and product use issue (spitting up the drug) were reported more frequently (15% and 10%, respectively; all Grade 1 or 2) compared to subjects 6 years of age and older. Five subjects (12%) discontinued treatment after vomiting or spitting up the drug [see Dosage and Administration (2.4, 2.5), Adverse Reactions (6.1), Clinical Pharmacology (12.3), and Clinical Studies (14.8)].

The safety and effectiveness of EPCLUSA for treatment of HCV genotype 5 in pediatric patients 3 years of age and older without cirrhosis or with compensated cirrhosis are supported by sofosbuvir, GS-331007, and velpatasvir exposures in adults and pediatric patients [see Dosage and Administration (2.2 and 2.4), Adverse Reactions (6.1), Clinical Pharmacology (12.3), and Clinical Studies (14.8)]. Similar rationale is used to support dosing recommendations for pediatric patients with HCV genotype 1, 2, 3, 4, 5, or 6 infection who have decompensated cirrhosis (Child-Pugh B or C).

In patients with severe renal impairment, including those requiring dialysis, exposures of GS-331007, the inactive metabolite of sofosbuvir, are increased [see Clinical Pharmacology (12.3)]. No data are available regarding the safety of EPCLUSA in pediatric patients with renal impairment [see Use in Specific Populations (8.6)].

The safety and effectiveness of EPCLUSA have not been established in pediatric patients less than 3 years of age.

8.5 Geriatric Use

Clinical trials of EPCLUSA included 156 subjects aged 65 and over (12% of total number of subjects in the Phase 3 clinical trials). No overall differences in safety or effectiveness were observed between these subjects and younger subjects, and other reported clinical experience has not identified differences in responses between the elderly and younger patients, but greater sensitivity of some older individuals cannot be ruled out. No dosage adjustment of EPCLUSA is warranted in geriatric patients [see Clinical Pharmacology (12.3)].

8.6 Renal Impairment

No dosage adjustment of EPCLUSA is recommended for patients with mild, moderate, or severe renal impairment, including ESRD requiring dialysis [see Dosage and Administration (2.6), Adverse Reactions (6.1), Clinical Pharmacology (12.3), and Clinical Studies (14.6)]. No safety data are available in subjects with both decompensated cirrhosis and severe renal impairment, including ESRD requiring dialysis. Additionally, no safety data are available in pediatric patients with renal impairment [see Use in Specific Populations (8.4)]. Refer to ribavirin tablet prescribing information regarding use of ribavirin in patients with renal impairment.

8.7 Hepatic Impairment

No dosage adjustment of EPCLUSA is recommended for patients with mild, moderate, or severe hepatic impairment (Child-Pugh Class A, B, or C) [see Adverse Reactions (6.1), Clinical Pharmacology (12.3), and Clinical Studies (14)].

Clinical and hepatic laboratory monitoring (including direct bilirubin), as clinically indicated, is recommended for patients with decompensated cirrhosis receiving treatment with EPCLUSA and ribavirin [see Adverse Reactions (6.1)].

8.8 People Who Inject Drugs (PWID), Including Those on Medication-Assisted Treatment (MAT) for Opioid Use Disorder

Based on data from the Phase 2 trial SIMPLIFY, the safety and effectiveness of EPCLUSA in subjects who self-reported injection drug use, including in those on concomitant MAT, were similar to the known safety and effectiveness profile of EPCLUSA. No dosage adjustment of EPCLUSA is recommended for PWID, including those on MAT for opioid use disorder [see Adverse Reactions (6.1) and Clinical Studies (14.7)].

10 OVERDOSAGE

No specific antidote is available for overdose with EPCLUSA. If overdose occurs the patient must be monitored for evidence of toxicity. Treatment of overdose with EPCLUSA consists of general supportive measures including monitoring of vital signs as well as observation of the clinical status of the patient. Hemodialysis can efficiently remove the predominant circulating metabolite of sofosbuvir, GS-331007, with an extraction ratio of 53%. Hemodialysis is unlikely to result in significant removal of velpatasvir since velpatasvir is highly bound to plasma protein.

11 DESCRIPTION

Tablets

EPCLUSA is a fixed-dose combination tablet containing sofosbuvir and velpatasvir for oral administration. Sofosbuvir is a nucleotide analog HCV NS5B polymerase inhibitor and velpatasvir is an NS5A inhibitor.

Each 400 mg/100 mg tablet contains 400 mg sofosbuvir and 100 mg velpatasvir, and each 200 mg/50 mg tablet contains 200 mg sofosbuvir and 50 mg velpatasvir. The tablets include the following inactive ingredients: copovidone, croscarmellose sodium, magnesium stearate, and microcrystalline cellulose. The tablets are film-coated with a coating material containing the following inactive ingredients: iron oxide red, polyethylene glycol, polyvinyl alcohol, talc, and titanium dioxide.

Pellets

EPCLUSA oral pellets are for oral administration, supplied as small, white to off-white pellets in unit-dose packets. Each unit-dose of EPCLUSA oral pellets contains either 200 mg sofosbuvir and 50 mg velpatasvir or 150 mg sofosbuvir and 37.5 mg velpatasvir and the following inactive ingredients: colloidal silicon dioxide, copovidone, croscarmellose sodium, lactose monohydrate, magnesium stearate, and microcrystalline cellulose. The oral pellets are film-coated with a coating material containing the following inactive ingredients: amino methacrylate copolymer, colloidal silicon dioxide, hypromellose, L-tartaric acid, polyethylene glycol, stearic acid, talc, and titanium dioxide.

Sofosbuvir: The IUPAC name for sofosbuvir is (S)-isopropyl 2-((S)-(((2R,3R,4R,5R)-5-(2,4-dioxo-3,4-dihydropyrimidin-1(2H)-yl)-4-fluoro-3-hydroxy-4-methyltetrahydrofuran-2-yl)methoxy)-(phenoxy)phosphorylamino)propanoate. It has a molecular formula of C22H29FN3O9P and a molecular weight of 529.45. It has the following structural formula:

Sofosbuvir is a white to off-white crystalline solid with a solubility of at least 2 mg/mL across the pH range of 2–7.7 at 37 °C and is slightly soluble in water.

Velpatasvir: The IUPAC name for velpatasvir is methyl {(1R)-2-[(2S,4S)-2-(5-{2-[(2S,5S)-1-{(2S)-2-[(methoxycarbonyl)amino]-3-methylbutanoyl}-5-methylpyrrolidin-2-yl]-1,11-dihydro[2]benzopyrano[4',3':6,7]naphtho[1,2-d]imidazol-9-yl}-1H-imidazol-2-yl)-4-(methoxymethyl)pyrrolidin-1-yl]-2-oxo-1-phenylethyl}carbamate. It has a molecular formula of C49H54N8O8 and a molecular weight of 883.0. It has the following structural formula:

Velpatasvir is practically insoluble (less than 0.1 mg/mL) above pH 5, slightly soluble (3.6 mg/mL) at pH 2, and soluble (greater than 36 mg/mL) at pH 1.2.

12 CLINICAL PHARMACOLOGY

12.1 Mechanism of Action

EPCLUSA is a fixed-dose combination of sofosbuvir and velpatasvir, which are direct-acting antiviral agents against the hepatitis C virus [see Microbiology (12.4)].

12.2 Pharmacodynamics

Cardiac Electrophysiology

The effect of sofosbuvir 400 mg (recommended dosage) and 1200 mg (3 times the recommended dosage) on QTc interval was evaluated in an active-controlled (moxifloxacin 400 mg) thorough QT trial. At a dose 3 times the recommended dose, sofosbuvir does not prolong QTc to any clinically relevant extent.

The effect of velpatasvir 500 mg (5 times the recommended dosage) was evaluated in an active-controlled (moxifloxacin 400 mg) thorough QT trial. At a dose 5 times the recommended dose, velpatasvir does not prolong QTc interval to any clinically relevant extent.

12.3 Pharmacokinetics

The pharmacokinetic properties of the components of EPCLUSA are provided in Table 5. The multiple dose pharmacokinetic parameters of sofosbuvir and its metabolite, GS-331007, and velpatasvir are provided in Table 6.

Table 5 Pharmacokinetic Properties of the Components of EPCLUSA
 | Sofosbuvir | Velpatasvir
Absorption
Tmax (hr) | 0.5–1 | 3
Effect of moderate meal (relative to fasting) [Values refer to mean systemic exposure. Moderate meal = ~600 kcal, 30% fat; high fat meal = ~800 kcal, 50% fat. EPCLUSA can be taken with or without food.] | ↑ 60% | ↑ 34%
Effect of high fat meal (relative to fasting) | ↑ 78% | ↑ 21%
Distribution
% Bound to human plasma proteins | 61–65 | >99.5
Blood-to-plasma ratio | 0.7 | 0.52–0.67
Metabolism
Metabolism | Cathepsin A CES1 HINT1 | CYP2B6 CYP2C8 CYP3A4
Elimination
Major route of elimination | SOF: metabolism GS-331007 [GS-331007 is the primary circulating nucleoside metabolite of SOF.] : glomerular filtration and active tubular secretion | Biliary excretion as parent (77%)
t1/2 (hr) [t1/2 values refer to median terminal plasma half-life.] | SOF: 0.5 GS-331007: 25 | 15
% Of dose excreted in urine [Single dose administration of [^14C] SOF or [^14C] VEL in mass balance studies.] | 80 [Predominantly as GS-331007.] | 0.4
% Of dose excreted in feces | 14 | 94
CES1 = carboxylesterase 1; HINT1 = histidine triad nucleotide-binding protein 1.

Table 6 Multiple Dose Pharmacokinetic Parameters of Sofosbuvir and its Metabolite, GS-331007, and Velpatasvir Following Oral Administration of EPCLUSA in HCV-Infected Adults
Parameter Mean (%CV) | Sofosbuvir [From Population PK analysis, N = 666] | GS-331007 [From Population PK analysis, N = 1029] | Velpatasvir [From Population PK analysis, N = 1025]
Cmax (ng/mL) | 567 (30.7) | 898 (26.7) | 259 (54.3)
AUCtau (ng∙hr/mL) | 1268 (38.5) | 14372 (28.0) | 2980 (51.3)
Ctrough (ng/mL) | NA | - | 42 (67.3)
CV = coefficient of variation; NA = not applicable.

Sofosbuvir and GS-331007 AUC0–24 and Cmax were similar in healthy adult subjects and subjects with HCV infection. Relative to healthy subjects (N=331), velpatasvir AUC0–24 and Cmax were 37% lower and 42% lower, respectively, in HCV-infected subjects.

Velpatasvir AUC increases in a greater than proportional manner from 5 to 50 mg and in a less than proportional manner from 50 to 450 mg in healthy volunteers. However, velpatasvir exhibited more than or near dose-proportional increase in exposures 25 mg to 150 mg in HCV-infected patients when coadministered with sofosbuvir. Sofosbuvir and GS-331007 AUCs are near dose-proportional over the dose range of 200 mg to 1200 mg.

Specific Populations

Pediatric Patients: The pharmacokinetics of sofosbuvir, GS-331007, and velpatasvir were determined in HCV genotype 1, 2, 3, 4, or 6 infected pediatric subjects 3 years of age and older receiving a daily dose of EPCLUSA as described below in Table 7. Sofosbuvir AUCtau and Cmax and velpatasvir Cmax values were 67%, 69%, and 78% higher in pediatric subjects ≥30 kg, 68%, 70%, and 96% higher in pediatric subjects 17 to <30 kg, and 103%, 135%, and 92% higher in pediatric subjects <17 kg compared to those observed in adults. These differences were not considered clinically significant. GS-331007 exposures and velpatasvir AUCtau and Ctau values in pediatric subjects were similar to those observed in adults.

Table 7 Exposures of Sofosbuvir, GS-331007, and Velpatasvir at Steady-State in HCV-Infected Pediatric Subjects 3 Years of Age and Older [Population PK derived parameters]
Weight Group | Dose | PK Parameter | Mean (%CV)
Weight Group | Dose | PK Parameter | Sofosbuvir | GS-331007 | Velpatasvir
<17 kg [Sofosbuvir N=11; GS-331007 N=11; Velpatasvir N=11] | 150/37.5 mg | Cmax (ng/mL) | 1550 (65.2) | 1090 (17.0) | 488 (46.6)
<17 kg [Sofosbuvir N=11; GS-331007 N=11; Velpatasvir N=11] | 150/37.5 mg | AUCtau (ng∙hr/mL) | 2830 (63.7) | 11900 (19.7) | 4480 (53.4)
<17 kg [Sofosbuvir N=11; GS-331007 N=11; Velpatasvir N=11] | 150/37.5 mg | Ctrough (ng/mL) | NA | - | 57.4 (82.7)
17 to <30 kg [Sofosbuvir N=62; GS-331007 N=64; Velpatasvir N=64] | 200/50 mg | Cmax (ng/mL) | 1200 (73.8) | 1070 (27.2) | 483 (39.5)
17 to <30 kg [Sofosbuvir N=62; GS-331007 N=64; Velpatasvir N=64] | 200/50 mg | AUCtau (ng∙hr/mL) | 2280 (55.6) | 11400 (43.3) | 4090 (38.5)
17 to <30 kg [Sofosbuvir N=62; GS-331007 N=64; Velpatasvir N=64] | 200/50 mg | Ctrough (ng/mL) | NA | - | 43 (65.8)
≥30 kg [Sofosbuvir N=90; GS-331007 N=101; Velpatasvir N=101] | 400/100 mg | Cmax (ng/mL) | 1310 (91.4) | 1180 (24.6) | 456 (56.4)
≥30 kg [Sofosbuvir N=90; GS-331007 N=101; Velpatasvir N=101] | 400/100 mg | AUCtau (ng∙hr/mL) | 2570 (82.8) | 13600 (27.6) | 4240 (46.7)
≥30 kg [Sofosbuvir N=90; GS-331007 N=101; Velpatasvir N=101] | 400/100 mg | Ctrough (ng/mL) | NA | - | 42.2 (66.4)
CV = coefficient of variation; NA = not applicable.

The pharmacokinetics of sofosbuvir, GS-331007 and velpatasvir have not been established in pediatric subjects less than 3 years of age [see Use in Specific Populations (8.4) and Clinical Studies (14.7)].

Geriatric Patients: Population pharmacokinetic analysis in HCV-infected subjects showed that within the age range (18 to 82 years) analyzed, age did not have a clinically relevant effect on the exposure to sofosbuvir, GS-331007, or velpatasvir [see Use in Specific Populations (8.5)].

Patients with Renal Impairment:

The pharmacokinetics of sofosbuvir were studied in HCV negative subjects with mild (eGFR between 50 to less than 80 mL/min/1.73 m^2), moderate (eGFR between 30 to less than 50 mL/min/1.73 m^2), severe renal impairment (eGFR less than 30 mL/min/1.73 m^2), and subjects with ESRD requiring hemodialysis following a single 400 mg dose of sofosbuvir. Relative to subjects with normal renal function (eGFR greater than 80 mL/min/1.73 m^2), the sofosbuvir AUC0–inf was 61%, 107%, and 171% higher in subjects with mild, moderate, and severe renal impairment, while the GS-331007 AUC0–inf was 55%, 88%, and 451% higher, respectively.

In subjects with ESRD, relative to subjects with normal renal function, sofosbuvir and GS-331007 AUC0–inf was 28% and 1280% higher when sofosbuvir was dosed 1 hour before hemodialysis compared with 60% and 2070% higher when sofosbuvir was dosed 1 hour after hemodialysis, respectively. A 4-hour hemodialysis session removed approximately 18% of administered dose [see Dosage and Administration (2.6) and Use in Specific Populations (8.6)].

The pharmacokinetics of velpatasvir were studied with a single dose of 100 mg velpatasvir in HCV negative subjects with severe renal impairment (eGFR less than 30 mL/min by Cockcroft-Gault). No clinically relevant differences in velpatasvir pharmacokinetics were observed between healthy subjects and subjects with severe renal impairment [see Use in Specific Populations (8.6)].

The pharmacokinetics of sofosbuvir, GS-331007, and velpatasvir were studied in HCV-infected subjects with ESRD requiring dialysis treated with EPCLUSA for 12 weeks. The results were generally consistent with those in HCV negative subjects with ESRD requiring dialysis.

Patients with Hepatic Impairment:

The pharmacokinetics of sofosbuvir were studied following 7-day dosing of 400 mg sofosbuvir in HCV-infected subjects with moderate and severe hepatic impairment (Child-Pugh Class B and C, respectively). Relative to subjects with normal hepatic function, the sofosbuvir AUC0–24 were 126% and 143% higher in moderate and severe hepatic impairment, while the GS-331007 AUC0–24 were 18% and 9% higher, respectively. Population pharmacokinetics analysis in HCV-infected subjects indicated that cirrhosis (including decompensated cirrhosis) had no clinically relevant effect on the exposure of sofosbuvir and GS-331007 [see Use in Specific Populations (8.7)].

The pharmacokinetics of velpatasvir were studied with a single dose of 100 mg velpatasvir in HCV negative subjects with moderate and severe hepatic impairment (Child-Pugh Class B and C). Velpatasvir plasma exposure (AUCinf) was similar in subjects with moderate hepatic impairment, severe hepatic impairment, and control subjects with normal hepatic function. Population pharmacokinetics analysis in HCV-infected subjects indicated that cirrhosis (including decompensated cirrhosis) had no clinically relevant effect on the exposure of velpatasvir [see Use in Specific Populations (8.7)].

Race: Population pharmacokinetics analysis in HCV-infected subjects indicated that race had no clinically relevant effect on the exposure of sofosbuvir, GS-331007, or velpatasvir.

Gender: Population pharmacokinetics analysis in HCV-infected subjects indicated that gender had no clinically relevant effect on the exposure of sofosbuvir, GS-331007, or velpatasvir.

Drug Interaction Studies

After oral administration of EPCLUSA, sofosbuvir is rapidly absorbed and subject to extensive first-pass hepatic extraction (hydrolysis followed by sequential phosphorylation) to form the pharmacologically active triphosphate. In clinical pharmacology studies, both sofosbuvir and the primary circulating metabolite GS-331007 (dephosphorylated nucleotide metabolite) were monitored for purposes of pharmacokinetic analyses.

Sofosbuvir and velpatasvir are substrates of drug transporters P-gp and BCRP while GS-331007 is not. Velpatasvir is also transported by OATP1B1 and OATP1B3. In vitro, slow metabolic turnover of velpatasvir by CYP2B6, CYP2C8, and CYP3A4 was observed. Inducers of P-gp and/or moderate to strong inducers of CYP2B6, CYP2C8, or CYP3A4 (e.g., rifampin, St. John's wort, carbamazepine) may decrease plasma concentrations of sofosbuvir and/or velpatasvir, leading to reduced therapeutic effect of EPCLUSA [see Warnings and Precautions (5.3) and Drug Interactions (7.3)]. Coadministration with drugs that inhibit P-gp and/or BCRP may increase sofosbuvir and/or velpatasvir plasma concentrations without increasing GS-331007 plasma concentration. Drugs that inhibit CYP2B6, CYP2C8, or CYP3A4 may increase plasma concentration of velpatasvir.

Velpatasvir is an inhibitor of drug transporter P-gp, BCRP, OATP1B1, OATP1B3, and OATP2B1, and its involvement in drug interactions with these transporters is primarily limited to the process of absorption. At clinically relevant concentration, velpatasvir is not an inhibitor of hepatic transporters OATP1A2 or OCT1, renal transporters OCT2, OAT1, OAT3, or MATE1, or CYP or UGT1A1 enzymes.

Sofosbuvir and GS-331007 are not inhibitors of drug transporters P-gp, BCRP, OATP1B1, OATP1B3, and OCT1 and GS-331007 is not an inhibitor of OAT1, OAT3, OCT2, and MATE1. Sofosbuvir and GS-331007 are not inhibitors or inducers of CYP or UGT1A1 enzymes.

The effects of coadministered drugs on the exposure of sofosbuvir, GS-331007, and velpatasvir are shown in Table 8. The effects of sofosbuvir, velpatasvir, or EPCLUSA on the exposure of coadministered drugs are shown in Table 9 [see Drug Interactions (7)].

Table 8 Drug Interactions: Changes in Pharmacokinetic Parameters for Sofosbuvir, GS-331007, and Velpatasvir in the Presence of the Coadministered Drug [All interaction studies conducted in healthy volunteers.]
Coadministered Drug | Dose of Coadministered Drug (mg) | SOF Dose (mg) | VEL Dose (mg) | N | Mean Ratio (90% CI) of Sofosbuvir, GS-331007, and Velpatasvir PK With/Without Coadministered Drug No Effect=1.00
Coadministered Drug | Dose of Coadministered Drug (mg) | SOF Dose (mg) | VEL Dose (mg) | N |  | Cmax | AUC | Cmin
Atazanavir/ ritonavir + emtricitabine/ tenofovir DF | 300/100 + 200/300 once daily | 400 once daily | 100 once daily | 24 | sofosbuvir | 1.12 (0.97, 1.29) | 1.22 (1.12, 1.33) | NA
Atazanavir/ ritonavir + emtricitabine/ tenofovir DF | 300/100 + 200/300 once daily | 400 once daily | 100 once daily | 24 | GS-331007 | 1.21 (1.12, 1.29) | 1.32 (1.27, 1.36) | 1.42 (1.37, 1.49)
Atazanavir/ ritonavir + emtricitabine/ tenofovir DF | 300/100 + 200/300 once daily | 400 once daily | 100 once daily | 24 | velpatasvir | 1.55 (1.41, 1.71) | 2.42 (2.23, 2.64) | 4.01 (3.57, 4.50)
Carbamazepine | 300 twice daily | 400 single dose | ND | 24 | sofosbuvir | 0.52 (0.43, 0.62) | 0.52 (0.46, 0.59) | NA
Carbamazepine | 300 twice daily | 400 single dose | ND | 24 | GS-331007 | 1.04 (0.97, 1.11) | 0.99 (0.94, 1.04) | NA
Cyclosporine | 600 single dose | 400 single dose | ND | 19 | sofosbuvir | 2.54 (1.87, 3.45) | 4.53 (3.26, 6.30) | NA
Cyclosporine | 600 single dose | 400 single dose | ND | 19 | GS-331007 | 0.60 (0.53, 0.69) | 1.04 (0.90, 1.20) | NA
Cyclosporine | 600 single dose | ND | 100 single dose | 12 | velpatasvir | 1.56 (1.22, 2.01) | 2.03 (1.51, 2.71) | NA
Darunavir/ ritonavir + emtricitabine/ tenofovir DF | 800/100 + 200/300 once daily | 400 once daily | 100 once daily | 29 | sofosbuvir | 0.62 (0.54, 0.71) | 0.72 (0.66, 0.80) | NA
Darunavir/ ritonavir + emtricitabine/ tenofovir DF | 800/100 + 200/300 once daily | 400 once daily | 100 once daily | 29 | GS-331007 | 1.04 (0.99, 1.08) | 1.13 (1.08, 1.18) | 1.13 (1.06, 1.19)
Darunavir/ ritonavir + emtricitabine/ tenofovir DF | 800/100 + 200/300 once daily | 400 once daily | 100 once daily | 29 | velpatasvir | 0.76 (0.65, 0.89) | 0.84 (0.72, 0.98) | 1.01 (0.87, 1.18)
Efavirenz/ emtricitabine/ tenofovir DF [Administered as ATRIPLA® (efavirenz, emtricitabine, and tenofovir DF fixed-dose combination).] | 600/200/300 once daily | 400 once daily | 100 once daily | 14 | sofosbuvir | 1.38 (1.14, 1.67) | 0.97 (0.83, 1.14) | NA
Efavirenz/ emtricitabine/ tenofovir DF [Administered as ATRIPLA® (efavirenz, emtricitabine, and tenofovir DF fixed-dose combination).] | 600/200/300 once daily | 400 once daily | 100 once daily | 14 | GS-331007 | 0.86 (0.80, 0.93) | 0.90 (0.85, 0.96) | 1.01 (0.95, 1.07)
Efavirenz/ emtricitabine/ tenofovir DF [Administered as ATRIPLA® (efavirenz, emtricitabine, and tenofovir DF fixed-dose combination).] | 600/200/300 once daily | 400 once daily | 100 once daily | 14 | velpatasvir | 0.53 (0.43, 0.64) | 0.47 (0.39, 0.57) | 0.43 (0.36, 0.52)
Elvitegravir/ cobicistat/emtricitabine/tenofovir alafenamide [Administered as GENVOYA® (elvitegravir, cobicistat, emtricitabine, and tenofovir alafenamide fixed-dose combination).] | 150/150/200/10 once daily | 400 once daily | 100 once daily | 24 | sofosbuvir | 1.23 (1.07, 1.42) | 1.37 (1.24, 1.52) | NA
Elvitegravir/ cobicistat/emtricitabine/tenofovir alafenamide [Administered as GENVOYA® (elvitegravir, cobicistat, emtricitabine, and tenofovir alafenamide fixed-dose combination).] | 150/150/200/10 once daily | 400 once daily | 100 once daily | 24 | GS-331007 | 1.29 (1.25, 1.33) | 1.48 (1.43, 1.53) | 1.58 (1.52, 1.65)
Elvitegravir/ cobicistat/emtricitabine/tenofovir alafenamide [Administered as GENVOYA® (elvitegravir, cobicistat, emtricitabine, and tenofovir alafenamide fixed-dose combination).] | 150/150/200/10 once daily | 400 once daily | 100 once daily | 24 | velpatasvir | 1.30 (1.17, 1.45) | 1.50 (1.35, 1.66) | 1.60 (1.44, 1.78)
Elvitegravir/ cobicistat/emtricitabine/tenofovir DF [Administered as STRIBILD® (elvitegravir, cobicistat, emtricitabine, and tenofovir DF fixed-dose combination).] | 150/150/200/300 once daily | 400 once daily | 100 once daily | 24 | sofosbuvir | 1.01 (0.85, 1.19) | 1.24 (1.13, 1.37) | NA
Elvitegravir/ cobicistat/emtricitabine/tenofovir DF [Administered as STRIBILD® (elvitegravir, cobicistat, emtricitabine, and tenofovir DF fixed-dose combination).] | 150/150/200/300 once daily | 400 once daily | 100 once daily | 24 | GS-331007 | 1.13 (1.07, 1.18) | 1.35 (1.30, 1.40) | 1.45 (1.38, 1.52)
Elvitegravir/ cobicistat/emtricitabine/tenofovir DF [Administered as STRIBILD® (elvitegravir, cobicistat, emtricitabine, and tenofovir DF fixed-dose combination).] | 150/150/200/300 once daily | 400 once daily | 100 once daily | 24 | velpatasvir | 1.05 (0.93, 1.19) | 1.19 (1.07, 1.34) | 1.37 (1.22, 1.54)
Famotidine | 40 single dose simultaneously with EPCLUSA | 400 single dose | 100 single dose | 60 | sofosbuvir | 0.92 (0.82, 1.05) | 0.82 (0.74, 0.91) | NA
Famotidine | 40 single dose simultaneously with EPCLUSA | 400 single dose | 100 single dose | 60 | GS-331007 | 0.84 (0.78, 0.89) | 0.94 (0.91, 0.98) | NA
Famotidine | 40 single dose simultaneously with EPCLUSA | 400 single dose | 100 single dose | 60 | velpatasvir | 0.80 (0.70, 0.91) | 0.81 (0.71, 0.91) | NA
Famotidine | 40 single dose 12 hours prior to EPCLUSA | 400 single dose | 100 single dose | 60 | sofosbuvir | 0.77 (0.68, 0.87) | 0.80 (0.73, 0.88) | NA
Famotidine | 40 single dose 12 hours prior to EPCLUSA | 400 single dose | 100 single dose | 60 | GS-331007 | 1.20 (1.13, 1.28) | 1.04 (1.01, 1.08) | NA
Famotidine | 40 single dose 12 hours prior to EPCLUSA | 400 single dose | 100 single dose | 60 | velpatasvir | 0.87 (0.76, 1.00) | 0.85 (0.74, 0.97) | NA
Ketoconazole | 200 twice daily | ND | 100 single dose | 12 | velpatasvir | 1.29 (1.02, 1.64) | 1.71 (1.35, 2.18) | NA
Lopinavir/ ritonavir + emtricitabine/ tenofovir DF | 4×200/50 + 200/300 once daily | 400 once daily | 100 once daily | 24 | sofosbuvir | 0.59 (0.49, 0.71) | 0.71 (0.64, 0.78) | NA
Lopinavir/ ritonavir + emtricitabine/ tenofovir DF | 4×200/50 + 200/300 once daily | 400 once daily | 100 once daily | 24 | GS-331007 | 1.01 (0.98, 1.05) | 1.15 (1.09, 1.21) | 1.15 (1.07, 1.25)
Lopinavir/ ritonavir + emtricitabine/ tenofovir DF | 4×200/50 + 200/300 once daily | 400 once daily | 100 once daily | 24 | velpatasvir | 0.70 (0.59, 0.83) | 1.02 (0.89, 1.17) | 1.63 (1.43, 1.85)
Methadone | 30 to 130 daily | 400 once daily | ND | 14 | sofosbuvir | 0.95 (0.68, 1.33) | 1.30 (1.00, 1.69) | NA
Methadone | 30 to 130 daily | 400 once daily | ND | 14 | GS-331007 | 0.73 (0.65, 0.83) | 1.04 (0.89, 1.22) | NA
Omeprazole | 20 once daily simultaneously with EPCLUSA | 400 single dose fasted | 100 single dose fasted | 60 | sofosbuvir | 0.66 (0.55, 0.78) | 0.71 (0.60, 0.83) | NA
Omeprazole | 20 once daily simultaneously with EPCLUSA | 400 single dose fasted | 100 single dose fasted | 60 | GS-331007 | 1.18 (1.10, 1.26) | 1.00 (0.95, 1.05) | NA
Omeprazole | 20 once daily simultaneously with EPCLUSA | 400 single dose fasted | 100 single dose fasted | 60 | velpatasvir | 0.63 (0.50, 0.78) | 0.64 (0.52, 0.79) | NA
Omeprazole | 20 once daily 12 hours prior to EPCLUSA | 400 single dose fasted | 100 single dose fasted | 60 | sofosbuvir | 0.55 (0.47, 0.64) | 0.56 (0.49, 0.65) | NA
Omeprazole | 20 once daily 12 hours prior to EPCLUSA | 400 single dose fasted | 100 single dose fasted | 60 | GS-331007 | 1.26 (1.18, 1.34) | 0.97 (0.94, 1.01) | NA
Omeprazole | 20 once daily 12 hours prior to EPCLUSA | 400 single dose fasted | 100 single dose fasted | 60 | velpatasvir | 0.43 (0.35, 0.54) | 0.45 (0.37, 0.55) | NA
Omeprazole | 20 once daily 2 hours prior to EPCLUSA | 400 single dose fed [EPCLUSA was administered under fasted conditions in the reference arms.] | 100 single dose fed | 40 | sofosbuvir | 0.84 (0.68, 1.03) | 1.08 (0.94, 1.25) | NA
Omeprazole | 20 once daily 2 hours prior to EPCLUSA | 400 single dose fed [EPCLUSA was administered under fasted conditions in the reference arms.] | 100 single dose fed | 40 | GS-331007 | 0.94 (0.88, 1.02) | 0.99 (0.96, 1.03) | NA
Omeprazole | 20 once daily 2 hours prior to EPCLUSA | 400 single dose fed [EPCLUSA was administered under fasted conditions in the reference arms.] | 100 single dose fed | 40 | velpatasvir | 0.52 (0.43, 0.64) | 0.62 (0.51, 0.75) | NA
Omeprazole | 20 once daily 4 hours after EPCLUSA | 400 single dose fed | 100 single dose fed | 38 | sofosbuvir | 0.79 (0.68, 0.92) | 1.05 (0.94, 1.16) | NA
Omeprazole | 20 once daily 4 hours after EPCLUSA | 400 single dose fed | 100 single dose fed | 38 | GS-331007 | 0.91 (0.85, 0.98) | 0.99 (0.95, 1.02) | NA
Omeprazole | 20 once daily 4 hours after EPCLUSA | 400 single dose fed | 100 single dose fed | 38 | velpatasvir | 0.67 (0.58, 0.78) | 0.74 (0.63, 0.86) | NA
Omeprazole | 40 once daily 4 hours after EPCLUSA | 400 single dose fed | 100 single dose fed | 40 | sofosbuvir | 0.70 (0.57, 0.87) | 0.91 (0.76, 1.08) | NA
Omeprazole | 40 once daily 4 hours after EPCLUSA | 400 single dose fed | 100 single dose fed | 40 | GS-331007 | 1.01 (0.96, 1.07) | 0.99 (0.94, 1.03) | NA
Omeprazole | 40 once daily 4 hours after EPCLUSA | 400 single dose fed | 100 single dose fed | 40 | velpatasvir | 0.44 (0.34, 0.57) | 0.47 (0.37, 0.60) | NA
Rifabutin | 300 once daily | 400 single dose | ND | 20 | sofosbuvir | 0.64 (0.53, 0.77) | 0.76 (0.63, 0.91) | NA
Rifabutin | 300 once daily | 400 single dose | ND | 20 | GS-331007 | 1.15 (1.03, 1.27) | 1.03 (0.95, 1.12) | NA
Rifampin | 600 once daily | 400 single dose | ND | 17 | sofosbuvir | 0.23 (0.19, 0.29) | 0.28 (0.24, 0.32) | NA
Rifampin | 600 once daily | 400 single dose | ND | 17 | GS-331007 | 1.23 (1.14, 1.34) | 0.95 (0.88, 1.03) | NA
Rifampin | 600 once daily | ND | 100 single dose | 12 | velpatasvir | 0.29 (0.23, 0.37) | 0.18 (0.15, 0.22) | NA
Rifampin | 600 single dose | ND | 100 single dose | 12 | velpatasvir | 1.28 (1.05, 1.56) | 1.46 (1.17, 1.83) | NA
Tacrolimus | 5 single dose | 400 single dose | ND | 16 | sofosbuvir | 0.97 (0.65, 1.43) | 1.13 (0.81, 1.57) | NA
Tacrolimus | 5 single dose | 400 single dose | ND | 16 | GS-331007 | 0.97 (0.83, 1.14) | 1.00 (0.87, 1.13) | NA
NA = not available/not applicable, ND = not dosed, DF = disoproxil fumarate.

No effect on the pharmacokinetic parameters of sofosbuvir, GS-331007, or velpatasvir was observed with dolutegravir; the combination of emtricitabine, rilpivirine, and tenofovir DF; emtricitabine; raltegravir; or tenofovir DF.

Table 9 Changes in Pharmacokinetic Parameters for Coadministered Drug in the Presence of Sofosbuvir, Velpatasvir, or EPCLUSA [All interaction studies conducted in healthy volunteers.]
Coadministered Drug | Dose of Coadministered Drug (mg) | SOF Dose (mg) | VEL Dose (mg) | N | Mean Ratio (90% CI) of Coadministered Drug PK With/Without Sofosbuvir, Velpatasvir, or EPCLUSA No Effect=1.00
Coadministered Drug | Dose of Coadministered Drug (mg) | SOF Dose (mg) | VEL Dose (mg) | N | Cmax | AUC | Cmin
Atazanavir/ ritonavir + emtricitabine/ tenofovir DF [Comparison based on exposures when administered as atazanavir/ritonavir + emtricitabine/tenofovir DF.] | atazanavir 300 once daily | 400 once daily | 100 once daily | 24 | 1.09 (1.00, 1.19) | 1.20 (1.10, 1.31) | 1.39 (1.20, 1.61)
Atazanavir/ ritonavir + emtricitabine/ tenofovir DF [Comparison based on exposures when administered as atazanavir/ritonavir + emtricitabine/tenofovir DF.] | ritonavir 100 once daily | 400 once daily | 100 once daily | 24 | 0.89 (0.82, 0.97) | 0.97 (0.89, 1.05) | 1.29 (1.15, 1.44)
Atazanavir/ ritonavir + emtricitabine/ tenofovir DF [Comparison based on exposures when administered as atazanavir/ritonavir + emtricitabine/tenofovir DF.] | emtricitabine 200 once daily | 400 once daily | 100 once daily | 24 | 1.01 (0.96, 1.06) | 1.02 (0.99, 1.04) | 1.06 (1.02, 1.11)
Atazanavir/ ritonavir + emtricitabine/ tenofovir DF [Comparison based on exposures when administered as atazanavir/ritonavir + emtricitabine/tenofovir DF.] | tenofovir DF 300 once daily | 400 once daily | 100 once daily | 24 | 1.55 (1.43, 1.68) | 1.30 (1.24, 1.36) | 1.39 (1.31, 1.48)
Atorvastatin | 40 single dose | 400 once daily | 100 once daily | 26 | 1.68 (1.49, 1.89) | 1.54 (1.45, 1.64) | NA
Darunavir/ ritonavir + emtricitabine/ tenofovir DF [Comparison based on exposures when administered as darunavir/ritonavir + emtricitabine/tenofovir DF.] | darunavir 800 once daily | 400 once daily | 100 once daily | 29 | 0.90 (0.86, 0.95) | 0.92 (0.87, 0.98) | 0.87 (0.79, 0.95)
Darunavir/ ritonavir + emtricitabine/ tenofovir DF [Comparison based on exposures when administered as darunavir/ritonavir + emtricitabine/tenofovir DF.] | ritonavir 100 once daily | 400 once daily | 100 once daily | 29 | 1.07 (0.97, 1.17) | 1.12 (1.05, 1.19) | 1.09 (1.02, 1.15)
Darunavir/ ritonavir + emtricitabine/ tenofovir DF [Comparison based on exposures when administered as darunavir/ritonavir + emtricitabine/tenofovir DF.] | emtricitabine 200 once daily | 400 once daily | 100 once daily | 29 | 1.05 (1.01, 1.08) | 1.05 (1.02, 1.08) | 1.04 (0.98, 1.09)
Darunavir/ ritonavir + emtricitabine/ tenofovir DF [Comparison based on exposures when administered as darunavir/ritonavir + emtricitabine/tenofovir DF.] | tenofovir DF 300 once daily | 400 once daily | 100 once daily | 29 | 1.55 (1.45, 1.66) | 1.39 (1.33, 1.44) | 1.52 (1.45, 1.59)
Digoxin | 0.25 single dose | ND | 100 | 21 | 1.88 (1.71, 2.08) | 1.34 (1.13, 1.60) | NA
Efavirenz/ emtricitabine/ tenofovir DF [Administered as ATRIPLA (efavirenz, emtricitabine, and tenofovir DF fixed-dose combination).] | efavirenz 600 once daily | 400 once daily | 100 once daily | 15 | 0.81 (0.74, 0.89) | 0.85 (0.80, 0.91) | 0.90 (0.85, 0.95)
Efavirenz/ emtricitabine/ tenofovir DF [Administered as ATRIPLA (efavirenz, emtricitabine, and tenofovir DF fixed-dose combination).] | emtricitabine 200 once daily | 400 once daily | 100 once daily | 15 | 1.07 (0.98, 1.18) | 1.07 (1.00, 1.14) | 1.10 (0.97, 1.25)
Efavirenz/ emtricitabine/ tenofovir DF [Administered as ATRIPLA (efavirenz, emtricitabine, and tenofovir DF fixed-dose combination).] | tenofovir DF 300 once daily | 400 once daily | 100 once daily | 15 | 1.77 (1.53, 2.04) | 1.81 (1.68, 1.94) | 2.21 (2.00, 2.43)
Elvitegravir/ cobicistat/emtricitabine/tenofovir alafenamide [Administered as GENVOYA (elvitegravir, cobicistat, emtricitabine, and tenofovir alafenamide fixed-dose combination).] | elvitegravir 150 once daily | 400 once daily | 100 once daily | 24 | 0.87 (0.80, 0.94) | 0.94 (0.88, 1.00) | 1.08 (0.97, 1.20)
Elvitegravir/ cobicistat/emtricitabine/tenofovir alafenamide [Administered as GENVOYA (elvitegravir, cobicistat, emtricitabine, and tenofovir alafenamide fixed-dose combination).] | cobicistat 150 once daily | 400 once daily | 100 once daily | 24 | 1.16 (1.09, 1.23) | 1.30 (1.23, 1.38) | 2.03 (1.67, 2.48)
Elvitegravir/ cobicistat/emtricitabine/tenofovir alafenamide [Administered as GENVOYA (elvitegravir, cobicistat, emtricitabine, and tenofovir alafenamide fixed-dose combination).] | emtricitabine 200 once daily | 400 once daily | 100 once daily | 24 | 1.02 (0.97, 1.06) | 1.01 (0.98, 1.04) | 1.02 (0.97, 1.07)
Elvitegravir/ cobicistat/emtricitabine/tenofovir alafenamide [Administered as GENVOYA (elvitegravir, cobicistat, emtricitabine, and tenofovir alafenamide fixed-dose combination).] | tenofovir alafenamide 10 once daily | 400 once daily | 100 once daily | 24 | 0.80 (0.68, 0.94) | 0.87 (0.81, 0.94) | NA
Elvitegravir/ cobicistat/emtricitabine/tenofovir DF [Administered as STRIBILD (elvitegravir, cobicistat, emtricitabine, and tenofovir DF fixed-dose combination).] | elvitegravir 150 once daily | 400 once daily | 100 once daily | 24 | 0.93 (0.86, 1.00) | 0.93 (0.87, 0.99) | 0.97 (0.91, 1.04)
Elvitegravir/ cobicistat/emtricitabine/tenofovir DF [Administered as STRIBILD (elvitegravir, cobicistat, emtricitabine, and tenofovir DF fixed-dose combination).] | cobicistat 150 once daily | 400 once daily | 100 once daily | 24 | 1.11 (1.06, 1.17) | 1.23 (1.17, 1.29) | 1.71 (1.54, 1.90)
Elvitegravir/ cobicistat/emtricitabine/tenofovir DF [Administered as STRIBILD (elvitegravir, cobicistat, emtricitabine, and tenofovir DF fixed-dose combination).] | emtricitabine 200 once daily | 400 once daily | 100 once daily | 24 | 1.02 (0.97, 1.08) | 1.01 (0.98, 1.04) | 1.06 (1.01, 1.11)
Elvitegravir/ cobicistat/emtricitabine/tenofovir DF [Administered as STRIBILD (elvitegravir, cobicistat, emtricitabine, and tenofovir DF fixed-dose combination).] | tenofovir DF 300 once daily | 400 once daily | 100 once daily | 24 | 1.36 (1.25, 1.47) | 1.35 (1.29, 1.42) | 1.45 (1.39, 1.51)
Emtricitabine/ rilpivirine/ tenofovir DF [Administered as COMPLERA® (emtricitabine, rilpivirine, and tenofovir DF fixed-dose combination).] | emtricitabine 200 once daily | 400 once daily | 100 once daily | 24 | 0.95 (0.90, 1.00) | 0.99 (0.97, 1.02) | 1.05 (0.99, 1.11)
Emtricitabine/ rilpivirine/ tenofovir DF [Administered as COMPLERA® (emtricitabine, rilpivirine, and tenofovir DF fixed-dose combination).] | rilpivirine 25 once daily | 400 once daily | 100 once daily | 24 | 0.93 (0.88, 0.98) | 0.95 (0.90, 1.00) | 0.96 (0.90, 1.03)
Emtricitabine/ rilpivirine/ tenofovir DF [Administered as COMPLERA® (emtricitabine, rilpivirine, and tenofovir DF fixed-dose combination).] | tenofovir DF 300 once daily | 400 once daily | 100 once daily | 24 | 1.44 (1.33, 1.55) | 1.40 (1.34, 1.46) | 1.84 (1.76, 1.92)
Norelgestromin | norgestimate 0.180/0.215/0.25/ethinyl estradiol 0.025 once daily | ND | 100 once daily | 13 | 0.97 (0.88, 1.07) | 0.90 (0.82, 0.98) | 0.92 (0.83, 1.03)
Norelgestromin | norgestimate 0.180/0.215/0.25/ethinyl estradiol 0.025 once daily | 400 once daily | ND | 15 | 1.07 (0.94, 1.22) | 1.06 (0.92, 1.21) | 1.07 (0.89, 1.28)
Norgestrel | norgestimate 0.180/0.215/0.25/ethinyl estradiol 0.025 once daily | ND | 100 once daily | 13 | 0.96 (0.78, 1.19) | 0.91 (0.73, 1.15) | 0.92 (0.73, 1.18)
Norgestrel | norgestimate 0.180/0.215/0.25/ethinyl estradiol 0.025 once daily | 400 once daily | ND | 15 | 1.18 (0.99, 1.41) | 1.19 (0.98, 1.45) | 1.23 (1.00, 1.51)
Ethinyl estradiol | norgestimate 0.180/0.215/0.25/ethinyl estradiol 0.025 once daily | ND | 100 once daily | 12 | 1.39 (1.17, 1.66) | 1.04 (0.87, 1.24) | 0.83 (0.65, 1.06)
Ethinyl estradiol | norgestimate 0.180/0.215/0.25/ethinyl estradiol 0.025 once daily | 400 once daily | ND | 15 | 1.15 (0.97, 1.36) | 1.09 (0.94, 1.26) | 0.99 (0.80, 1.23)
Pravastatin | 40 single dose | ND | 100 once daily | 18 | 1.28 (1.08, 1.52) | 1.35 (1.18, 1.54) | NA
Rosuvastatin | 10 single dose | ND | 100 once daily | 18 | 2.61 (2.32, 2.92) | 2.69 (2.46, 2.94) | NA
Raltegravir + emtricitabine/ tenofovir DF | emtricitabine 200 once daily | 400 once daily | 100 once daily | 30 | 1.08 (1.04, 1.12) | 1.05 (1.03, 1.07) | 1.02 (0.97, 1.08)
Raltegravir + emtricitabine/ tenofovir DF | tenofovir DF 300 once daily | 400 once daily | 100 once daily | 30 | 1.46 (1.39, 1.54) | 1.40 (1.34, 1.45) | 1.70 (1.61, 1.79)
Raltegravir + emtricitabine/ tenofovir DF | raltegravir 400 twice daily | 400 once daily | 100 once daily | 30 | 1.03 (0.74, 1.43) | 0.97 (0.73, 1.28) | 0.79 (0.42, 1.48)
Tacrolimus | 5 single dose | 400 single dose | ND | 16 | 0.73 (0.59, 0.90) | 1.09 (0.84, 1.40) | NA
NA = not available/not applicable, ND = not dosed, DF = disoproxil fumarate.

No effect on the pharmacokinetic parameters of the following coadministered drugs was observed or is expected with EPCLUSA (buprenorphine/naloxone, dolutegravir, lopinavir/ritonavir, or methadone) or its components sofosbuvir (cyclosporine) or velpatasvir (cyclosporine).

12.4 Microbiology

Mechanism of Action

Sofosbuvir is an inhibitor of the HCV NS5B RNA-dependent RNA polymerase, which is required for viral replication. Sofosbuvir is a nucleotide prodrug that undergoes intracellular metabolism to form the pharmacologically active uridine analog triphosphate (GS-461203), which can be incorporated into HCV RNA by the NS5B polymerase and acts as a chain terminator. In a biochemical assay, GS-461203 inhibited the polymerase activity of the recombinant NS5B from HCV genotype 1b, 2a, 3a, and 4a with an IC50 value ranging from 0.36 to 3.3 micromolar. GS-461203 is neither an inhibitor of human DNA and RNA polymerases nor an inhibitor of mitochondrial RNA polymerase.

Velpatasvir is an inhibitor of the HCV NS5A protein, which is required for viral replication. Resistance selection in cell culture and cross-resistance studies indicate velpatasvir targets NS5A as its mode of action.

Antiviral Activity

The EC50 values of sofosbuvir and velpatasvir against full-length or chimeric replicons encoding NS5B and NS5A sequences from the laboratory strains are presented in Table 10. The EC50 values of sofosbuvir and velpatasvir against clinical isolates are presented in Table 11.

Table 10 Activity of Sofosbuvir and Velpatasvir Against Full Length or Chimeric Laboratory Replicons
Replicon Genotype | Sofosbuvir EC50, nM [Mean value from multiple experiments of same laboratory replicon.] | Velpatasvir EC50, nM
1a | 40 | 0.014
1b | 110 | 0.016
2a | 50 | 0.005–0.016 [Data from various strains of full-length NS5A replicons or chimeric NS5A replicons carrying full-length NS5A genes that contain L31 or M31 polymorphisms.]
2b | 15 [Stable chimeric 1b replicons carrying NS5B genes from genotype 2b, 5a, or 6a were used for testing.] | 0.002–0.006
3a | 50 | 0.004
4a | 40 | 0.009
4d | 33.4 | 0.004
5a | 15 | 0.021–0.054 [Data from a chimeric NS5A replicon carrying NS5A amino acids 9–184.]
6a | 14–25 | 0.006–0.009
6e | NA | 0.130
NA = not available.

Table 11 Activity of Sofosbuvir and Velpatasvir Against Transient Replicons Containing NS5A or NS5B from Clinical Isolates
Replicon Genotype | Replicons Containing NS5B from Clinical Isolates |  | Replicons Containing NS5A from Clinical Isolates
Replicon Genotype | Number of clinical isolates | Median sofosbuvir EC50, nM (range) | Number of clinical isolates | Median velpatasvir EC50, nM (range)
1a | 67 | 62 (29–128) | 23 | 0.019 (0.011–0.078)
1b | 29 | 102 (45–170) | 34 | 0.012 (0.005–0.500)
2a | 1 | 28 | 8 | 0.011 (0.006–0.364)
2b | 14 | 30 (14–81) | 16 | 0.002 (0.0003–0.007)
3a | 106 | 81 (24–181) | 38 | 0.005 (0.002–1.871)
4a | NA | NA | 5 | 0.002 (0.001–0.004)
4d | NA | NA | 10 | 0.007 (0.004–0.011)
4r | NA | NA | 7 | 0.003 (0.002–0.006)
5a | NA | NA | 42 | 0.005 (0.001–0.019)
6a | NA | NA | 26 | 0.007 (0.0005–0.113)
6e | NA | NA | 15 | 0.024 (0.005–0.433)
NA = not available.

Velpatasvir was not antagonistic in reducing HCV RNA levels in replicon cells when combined with sofosbuvir or interferon-α, ribavirin, an HCV NS3/4A protease inhibitor, or HCV NS5B non-nucleoside inhibitors.

Resistance

In Cell Culture

HCV replicons with reduced susceptibility to sofosbuvir have been selected in cell culture for multiple genotypes including 1b, 2a, 2b, 3a, 4a, 5a, and 6a. Reduced susceptibility to sofosbuvir was associated with the NS5B substitution S282T in all replicon genotypes examined. An M289L substitution developed along with the S282T substitution in genotype 2a, 5, and 6 replicons. Site-directed mutagenesis of the S282T substitution in replicons of genotypes 1 to 6 conferred 2- to 18-fold reduced susceptibility to sofosbuvir.

HCV genotype 1a, 1b, 2a, 3a, 4a, 5a, and 6a replicon variants with reduced susceptibility to velpatasvir were selected in cell culture. Variants developed amino acid substitutions at NS5A resistance-associated positions 24, 28, 30, 31, 32, 58, 92, and 93. Phenotypic analysis of site-directed mutant replicons of the selected NS5A substitutions showed that single and double combinations of L31V and Y93H/N in genotype 1a, the combination of L31V + Y93H in genotype 1b, Y93H/S in genotype 3a, and L31V and P32A/L/Q/R in genotype 6 conferred greater than 100-fold reduction in velpatasvir susceptibility. In the genotype 2a replicon, the single mutants F28S and Y93H showed 91-fold and 46-fold reduced susceptibility to velpatasvir, respectively. The single mutant Y93H conferred 3-fold reduced susceptibility to velpatasvir in genotype 4a replicons. Combinations of these NS5A substitutions often showed greater reductions in susceptibility to velpatasvir than single substitutions alone.

In Clinical Trials

Studies in Subjects without Cirrhosis and Subjects with Compensated Cirrhosis

In a pooled analysis of subjects without cirrhosis or with compensated cirrhosis who received EPCLUSA for 12 weeks in Phase 3 trials (ASTRAL-1, ASTRAL-2, and ASTRAL-3), 12 subjects (2 with genotype 1 [1a, 1c/h] and 10 with genotype 3a) qualified for resistance analysis due to virologic failure. No subjects with genotype 2, 4, 5, or 6 HCV infection experienced virologic failure.

Of the 2 genotype 1 virologic failure subjects, 1 subject had virus with emergent NS5A resistance substitution Y93N and the other had virus with emergent NS5A resistance substitutions Y93H and low-level K24M/T and L31I/V at virologic failure. The latter subject had genotype 1c/h virus at baseline harboring NS5A resistance polymorphisms (Q30R, L31M, H58P) relative to genotype 1a. No sofosbuvir NS5B nucleoside analog resistance-associated substitutions were observed at failure in the 2 subjects.

Of the 10 genotype 3a virologic failure subjects, NS5A resistance substitution Y93H was observed in all 10 subjects at failure (7 subjects had Y93H emerge post-treatment and 3 subjects had Y93H at baseline and post-treatment). Treatment-emergent sofosbuvir NS5B substitutions L314F (n=2) and L314I (n=1) were observed at high frequency (greater than or equal to 15%) in the NS5B polymerase in 3 genotype 3a subjects who relapsed: one in the EPCLUSA group and two in the sofosbuvir plus ribavirin 24-week group. In addition, low frequency (less than 4%) treatment-emergent L314P was detected in 2 genotype 3a subjects who relapsed, including one subject in the sofosbuvir plus ribavirin 24-week group in ASTRAL-3 and one in the EPCLUSA group in ASTRAL-4. The clinical significance of this substitution is unknown.

In Trial 2104 (liver transplant recipients), there were 2 virologic failures (1 subject with genotype 1a and 1 subject with genotype 3b). The genotype 1a virologic failure subject had virus with an NS5A K24R polymorphism at baseline and relapse, and treatment-emergent NS5A L31V. The genotype 3b virologic failure subject had virus at baseline and relapse with NS5A polymorphisms A30K+L31M, which are predominant in this subtype; treatment-emergent NS5B S282T was detected at relapse.

Studies in Subjects with Decompensated Cirrhosis

In the ASTRAL-4 trial in subjects with decompensated cirrhosis who received EPCLUSA with ribavirin for 12 weeks, 3 subjects (1 with genotype 1a and 2 with genotype 3a) qualified for resistance analysis due to virologic failure. No subjects with genotype 2 or 4 HCV infection who received EPCLUSA with ribavirin for 12 weeks experienced virologic failure.

The genotype 1 virologic failure subject had no NS5A or NS5B resistance substitutions at failure.

The 2 genotype 3a virologic failure subjects had the NS5A resistance substitutions Y93H and either low-level M28V or S38P emerge at failure. One of these subjects also developed low levels (less than 5%) of NS5B nucleoside analog inhibitor resistance substitutions N142T and E237G at failure.

In the ASTRAL-4 trial, 2 subjects treated with EPCLUSA for 12 or 24 weeks without ribavirin had emergent sofosbuvir NS5B resistance-associated substitutions S282T at low levels (less than 5%) along with L159F. EPCLUSA for 12 or 24 weeks without ribavirin is not recommended in patients with decompensated cirrhosis.

Persistence of Resistance-Associated Substitutions

No data are available on the persistence of sofosbuvir or velpatasvir resistance-associated substitutions. NS5A resistance-associated substitutions observed with administration of other NS5A inhibitors have been found to persist for longer than 1 year in most patients. The long-term clinical impact of the emergence or persistence of virus containing sofosbuvir or velpatasvir resistance-associated substitutions is unknown.

Effect of Baseline HCV Polymorphisms on Treatment Response

Adults

Analyses were conducted to explore the association between relapse rates and pre-existing baseline NS5A resistance-associated polymorphisms (RAPs) (any change from reference at NS5A amino acid positions 24, 28, 30, 31, 58, 92, or 93) identified by population or deep sequencing analysis at a sensitivity threshold of 15% or higher for subjects without cirrhosis or with compensated cirrhosis in ASTRAL-1, ASTRAL-2, and ASTRAL-3 and subjects with decompensated cirrhosis in ASTRAL-4.

Studies in Subjects without Cirrhosis and Subjects with Compensated Cirrhosis

Among the subjects who received treatment with EPCLUSA for 12 weeks, 18% (37/209), 32% (38/117), 64% (149/232), 20% (56/274), 63% (73/115), 9% (3/34), and 83% (35/42) of subjects with genotype 1a, 1b, 2, 3, 4, 5, and 6 HCV, respectively, had baseline virus with NS5A RAPs.

Genotype 1: Among the 75 genotype 1 subjects who had baseline NS5A RAPs, one subject (1%) with Q30R, L31M, and H58P polymorphisms at baseline and compensated cirrhosis relapsed.

Genotype 3: Among the 56 genotype 3 subjects in ASTRAL-3 who had baseline NS5A RAPs, 4 subjects (7%) relapsed (3 with baseline Y93H and 1 with baseline A30K). Overall, 20% (3/15) of genotype 3 subjects with the Y93H polymorphism at baseline relapsed.

In a pooled analysis of clinical trials in subjects with HCV genotype 3 infection, the prevalence of the baseline NS5A Y93H polymorphism was 6% (104/1842). Among HCV genotype 3 infected subjects with the Y93H polymorphism who were treated with EPCLUSA for 12 weeks, 7% (2/28) of subjects without cirrhosis relapsed, and 40% (6/15) of subjects with compensated cirrhosis experienced virologic failure (5 relapse, 1 on-treatment).

Genotypes 2, 4, 5, and 6: The presence of baseline NS5A RAPs did not affect relapse rates for subjects with genotypes 2, 4, 5, and 6, because all achieved sustained virologic response (SVR) 12.

SVR12 was achieved in all 77 subjects who had baseline NS5B nucleoside analog inhibitor resistance polymorphisms including N142T, L159F, E/N237G, C/M289L/I, L320F/I/V, V321A/I, and S282G + V321I. The sofosbuvir NS5B nucleoside analog inhibitor resistance substitution S282T was not detected in the baseline NS5B sequence of any subject using 1% deep sequencing cutoff in Phase 3 trials.

Studies in Subjects with Decompensated Cirrhosis

In ASTRAL-4, the prevalence of NS5A RAPs at baseline was 24% (48/198), 60% (6/10), 11% (4/37), and 63% (5/8) in GT1, GT2, GT3, and GT4 HCV subjects, respectively. No subjects with genotypes 2, 4 and 6 relapsed. There were no subjects with genotype 5 in this trial.

For genotype 1 subjects, the overall relapse rates were numerically lower for the 12-week EPCLUSA with ribavirin group (2%; 1/66) compared to EPCLUSA 12-week and 24-week treatment groups. For subjects with NS5A RAPs, relapse rates were 0% (0/17) compared to 2% (1/49) for subjects without NS5A RAPs in the 12-week EPCLUSA with ribavirin containing group.

For genotype 3 subjects, overall virologic failure rates were numerically lower for the 12-week EPCLUSA with ribavirin group (15%; 2/13) compared to EPCLUSA 12-week and 24-week treatment groups. There are insufficient data to determine the impact of HCV NS5A RAPs in genotype 3 subjects with decompensated cirrhosis.

Three subjects in the EPCLUSA with ribavirin 12-week group had baseline NS5B nucleoside analog inhibitor polymorphisms (N142T and L159F) using 1% deep sequencing cutoff and all 3 subjects achieved SVR12.

Pediatrics

In Study 1143, the presence of NS5A and NS5B RAPs did not impact treatment outcome; all pediatric subjects 3 years of age and older with baseline NS5A RAPs (15%; 29/199) or NS5B nucleoside inhibitor RAPs (3%; 6/195) achieved SVR following 12 weeks treatment with EPCLUSA.

Cross Resistance

Both sofosbuvir and velpatasvir were fully active against substitutions associated with resistance to other classes of direct-acting antivirals with different mechanisms of action, such as NS5B non-nucleoside inhibitors and NS3 protease inhibitors. The efficacy of EPCLUSA has not been established in patients who have previously failed treatment with other regimens that include an NS5A inhibitor.

13 NONCLINICAL TOXICOLOGY

13.1 Carcinogenesis, Mutagenesis, Impairment of Fertility

Carcinogenesis and Mutagenesis

Sofosbuvir: Sofosbuvir was not genotoxic in a battery of in vitro or in vivo assays, including bacterial mutagenicity, chromosome aberration using human peripheral blood lymphocytes, and in vivo mouse micronucleus assays.

Sofosbuvir was not carcinogenic in a 2-year mouse study (up to 200 mg/kg/day in males and 600 mg/kg/day in females) and in a 2-year rat study (up to 750 mg/kg/day), resulting in exposures of the predominant circulating metabolite GS-331007 of approximately 3 and 15 times (in mice) and 7 and 9 times (in rats), in males and females, respectively, the exposure in humans at the recommended human dose (RHD).

Velpatasvir: Velpatasvir was not genotoxic in a battery of in vitro or in vivo assays, including bacterial mutagenicity, chromosome aberration using human peripheral blood lymphocytes, and in vivo rat micronucleus assays.

Velpatasvir was not carcinogenic in a 6-month rasH2 transgenic mouse study (up to 1000 mg/kg/day) and a 2-year rat carcinogenicity study (up to 200 mg/kg/day). The exposure of VEL in the 2-year rat study was approximately 6 times the exposure in humans at the RHD.

Impairment of Fertility

Sofosbuvir: Sofosbuvir had no effects on embryo-fetal viability or on fertility when evaluated in rats. At the highest dose tested, AUC exposure to the predominant circulating metabolite GS-331007 was approximately 4 times the exposure in humans at the RHD.

Velpatasvir: Velpatasvir had no effects on embryo-fetal viability or on fertility when evaluated in rats. At the highest dose tested, velpatasvir exposure was approximately 6 times the exposure in humans at the RHD.

14 CLINICAL STUDIES

14.1 Description of Clinical Trials

Table 12 presents the clinical trial design including different treatment groups that were conducted with EPCLUSA with and without ribavirin in subjects with chronic hepatitis C (HCV) genotype 1, 2, 3, 4, 5, and 6 infection. For detailed description of trial design and recommended regimen and duration [see Dosage and Administration (2.2, 2.3, and 2.4) and Clinical Studies (14.2, 14.3, 14.4, 14.5, 14.6, 14.7, and 14.8)].

Table 12 Trials Conducted with EPCLUSA in Subjects with Genotype 1, 2, 3, 4, 5, or 6 HCV Infection
Trial | Population | EPCLUSA and Comparator Groups (Number of Subjects Treated)
ASTRAL-1 [Double-blind, placebo-controlled.] (NCT02201940) | Genotype 1, 2, 4, 5, and 6 TN and TE [TE = treatment-experienced subjects are those who have failed a peginterferon alfa/ribavirin based regimen with or without an HCV protease inhibitor (boceprevir, simeprevir, or telaprevir).] , without cirrhosis or with compensated cirrhosis | EPCLUSA 12 weeks (624) Placebo 12 weeks (116)
ASTRAL-2 [Open-label.] (NCT02220998) | Genotype 2 TN and TE, without cirrhosis or with compensated cirrhosis | EPCLUSA 12 weeks (134) SOF + RBV 12 weeks (132)
ASTRAL-3 (NCT02201953) | Genotype 3 TN and TE, without cirrhosis or with compensated cirrhosis | EPCLUSA 12 weeks (277) SOF + RBV 24 weeks (275)
ASTRAL-5 (NCT02480712) | Genotype 1, 2, 3, 4, 5, and 6 HCV/HIV-1 coinfected TN and TE, without cirrhosis or with compensated cirrhosis | EPCLUSA 12 weeks (106)
ASTRAL-4 (NCT02201901) | Genotype 1, 2, 3, 4, 5, and 6 TN and TE, with CP class B decompensated cirrhosis | EPCLUSA 12 weeks (90) EPCLUSA + RBV 12 weeks (87) EPCLUSA 24 weeks (90)
2104 (NCT02781571) | Genotype 1, 2, 3, and 4 TN and TE [TE = treatment-experienced subjects are those who have failed a peginterferon alfa/ribavirin based regimen or an HCV-specific DAA-based regimen that does not include an NS5A inhibitor.] liver transplant recipients, without cirrhosis or with compensated cirrhosis | EPCLUSA 12 weeks (79)
4062 (NCT03036852) | Genotype 1, 2, 3, 4, and 6 TN and TE [TE = treatment-experienced subjects are those who have failed a peginterferon alfa/ribavirin or interferon/ribavirin based regimen.] without cirrhosis or with compensated cirrhosis, with ESRD requiring dialysis | EPCLUSA 12 weeks (59)
SIMPLIFY (NCT02336139) | Genotype 1, 2, 3, and 4 PWID, including those on MAT for opioid use disorder, without cirrhosis or with compensated cirrhosis | EPCLUSA 12 weeks (103)
1143 (NCT03022981) | Genotype 1, 2, 3, 4, and 6 TN and TE [TE = treatment-experienced subjects are those who have failed an interferon-based regimen with or without ribavirin and with or without an HCV protease inhibitor (boceprevir, simeprevir, or telaprevir).] pediatric subjects 3 years of age and older | EPCLUSA 12 weeks (214)
TN = treatment-naïve subjects; SOF = sofosbuvir; RBV = ribavirin; CP = Child-Pugh; ESRD = End Stage Renal Disease; PWID = People Who Inject Drugs; MAT = Medication-Assisted Treatment.

The ribavirin dosage was weight-based (1000 mg daily administered in two divided doses for subjects less than 75 kg and 1200 mg for those greater than or equal to 75 kg) and administered in two divided doses when used in combination with sofosbuvir in the ASTRAL-2 and ASTRAL-3 trials or in combination with EPCLUSA in the ASTRAL-4 trial. Ribavirin dosage adjustments were performed according to the ribavirin prescribing information. Serum HCV RNA values were measured during the clinical trials using the COBAS AmpliPrep/COBAS Taqman HCV test (version 2.0) with a lower limit of quantification (LLOQ) of 15 IU/mL. SVR12, defined as HCV RNA less than LLOQ at 12 weeks after the cessation of treatment, was the primary endpoint in all the trials. Relapse is defined as HCV RNA greater than or equal to LLOQ during the post-treatment period after having achieved HCV RNA less than LLOQ at the end of treatment. On-treatment virologic failure is defined as breakthrough, rebound, or non-response.

14.2 Clinical Trials in Subjects without Cirrhosis and Subjects with Compensated Cirrhosis

Genotype 1, 2, 4, 5, and 6 HCV Infected Adults (ASTRAL-1)

ASTRAL-1 was a randomized, double-blind, placebo-controlled trial that evaluated 12 weeks of treatment with EPCLUSA compared with 12 weeks of placebo in subjects with genotype 1, 2, 4, 5, or 6 HCV infection without cirrhosis or with compensated cirrhosis. Subjects with genotype 1, 2, 4, or 6 HCV infection were randomized in a 5:1 ratio to treatment with EPCLUSA or placebo for 12 weeks. Subjects with genotype 5 HCV infection were enrolled to the EPCLUSA group. Randomization was stratified by HCV genotype (1, 2, 4, 6, and indeterminate) and the presence or absence of compensated cirrhosis.

Demographics and baseline characteristics were balanced between the EPCLUSA and placebo group. Of the 740 treated subjects, the median age was 56 years (range: 18 to 82); 60% of the subjects were male; 79% were White, 9% were Black; 21% had a baseline body mass index at least 30 kg/m^2; the proportions of subjects with genotype 1, 2, 4, 5, or 6 HCV infection were 53%, 17%, 19%, 5%, and 7%, respectively; 69% had non-CC IL28B alleles (CT or TT); 74% had baseline HCV RNA levels at least 800,000 IU/mL; 19% had compensated cirrhosis; and 32% were treatment-experienced.

Table 13 presents SVR12 and other virologic outcomes in EPCLUSA-treated subjects in the ASTRAL-1 trial by HCV genotype. No subjects in the placebo group achieved SVR12.

Table 13 Study ASTRAL-1: Virologic Outcomes by HCV Genotype in EPCLUSA-Treated Subjects without Cirrhosis or with Compensated Cirrhosis (12 Weeks After Treatment)
 | EPCLUSA 12 Weeks (N=624)
 | Total (all GTs) (N=624) | GT-1 |  |  | GT-2 (N=104) | GT-4 (N=116) | GT-5 (N=35) | GT-6 (N=41)
 | Total (all GTs) (N=624) | GT-1a (N=210) | GT-1b (N=118) | Total (N=328) | GT-2 (N=104) | GT-4 (N=116) | GT-5 (N=35) | GT-6 (N=41)
SVR12 | 99% (618/624) | 98% (206/210) | 99% (117/118) | 98% (323/328) | 100% (104/104) | 100% (116/116) | 97% (34/35) | 100% (41/41)
Outcome for Subjects without SVR
On-Treatment Virologic Failure | 0/624 | 0/210 | 0/118 | 0/328 | 0/104 | 0/116 | 0/35 | 0/41
Relapse [The denominator for relapse is the number of subjects with HCV RNA <LLOQ at their last on-treatment assessment.] | <1% (2/623) | <1% (1/209) | 1% (1/118) | 1% (2/327) | 0/104 | 0/116 | 0/35 | 0/41
Other [Other includes subjects who did not achieve SVR and did not meet virologic failure criteria.] | 1% (4/624) | 1% (3/210) | 0/118 | 1% (3/328) | 0/104 | 0/116 | 3% (1/35) | 0/41
GT = genotype; no subjects in the placebo group achieved SVR12.

Genotype 2 HCV Infected Adults (ASTRAL-2)

ASTRAL-2 was a randomized, open-label trial that evaluated 12 weeks of treatment with EPCLUSA compared with 12 weeks of treatment with SOF with ribavirin in subjects with genotype 2 HCV infection. Subjects were randomized in a 1:1 ratio to the treatment groups. Randomization was stratified by the presence or absence of compensated cirrhosis and prior treatment experience (treatment-naïve vs treatment-experienced).

Demographics and baseline characteristics were balanced across the two treatment groups. Of the 266 treated subjects, the median age was 58 years (range: 23 to 81); 59% of the subjects were male; 88% were White; 7% were Black; 33% had a baseline body mass index at least 30 kg/m^2; 62% had non-CC IL28B alleles (CT or TT); 80% had baseline HCV RNA levels at least 800,000 IU/mL; 14% had compensated cirrhosis; and 15% were treatment-experienced.

Table 14 presents SVR12 and other virologic outcomes from the ASTRAL-2 trial.

Table 14 Study ASTRAL-2: Virologic Outcomes in Subjects with Genotype 2 HCV without Cirrhosis or with Compensated Cirrhosis (12 Weeks After Treatment)
 | EPCLUSA 12 Weeks (N=134) | SOF + RBV 12 Weeks (N=132)
SVR12 | 99% (133/134) | 94% (124/132)
 | Treatment difference +5.2%; 95% confidence interval (+0.2% to +10.3%)
Outcome for subjects without SVR
On-Treatment Virologic Failure | 0/134 | 0/132
Relapse [The denominator for relapse is the number of subjects with HCV RNA <LLOQ at the last on-treatment assessment.] | 0/133 | 5% (6/132)
Other [Other includes subjects who did not achieve SVR12 and did not meet virologic failure criteria.] | 1% (1/134) | 2% (2/132)
SOF = sofosbuvir; RBV = ribavirin.

Genotype 3 HCV Infected Adults (ASTRAL-3)

ASTRAL-3 was a randomized, open-label trial that evaluated 12 weeks of treatment with EPCLUSA compared with 24 weeks of treatment with SOF with ribavirin in subjects with genotype 3 HCV infection. Subjects were randomized in a 1:1 ratio to the treatment groups. Randomization was stratified by the presence or absence of compensated cirrhosis and prior treatment experience (treatment-naïve vs treatment-experienced).

Demographics and baseline characteristics were balanced across the treatment groups. Of the 552 treated subjects, the median age was 52 years (range: 19 to 76); 62% of the subjects were male; 89% were White; 9% were Asian; 20% had a baseline body mass index at least 30 kg/m^2; 61% had non-CC IL28B alleles (CT or TT); 70% had baseline HCV RNA levels at least 800,000 IU/mL; 30% had compensated cirrhosis; and 26% were treatment-experienced.

Table 15 presents SVR12 and other virologic outcomes from the ASTRAL-3 trial.

Table 15 Study ASTRAL-3: Virologic Outcomes in Subjects with Genotype 3 HCV without Cirrhosis or with Compensated Cirrhosis (12 Weeks After Treatment)
 | EPCLUSA 12 Weeks (N=277) | SOF + RBV 24 Weeks (N=275)
SVR12 | 95% (264/277) | 80% (221/275)
 | Treatment difference +14.8%; 95% confidence interval (+9.6% to +20.0%)
Outcome for subjects without SVR
On-Treatment Virologic Failure | 0/277 | <1% (1/275)
Relapse [The denominator for relapse is the number of subjects with HCV RNA <LLOQ at the last on-treatment assessment.] | 4% (11/276) | 14% (38/272)
Other [Other includes subjects who did not achieve SVR and did not meet virologic failure criteria.] | 1% (2/277) | 5% (15/275)
SOF = sofosbuvir; RBV = ribavirin.

SVR12 for selected subgroups are presented in Table 16.

Table 16 Study ASTRAL-3: SVR12 by Prior Treatment and Presence/Absence of Compensated Cirrhosis in Subjects with Genotype 3 HCV
 | EPCLUSA 12 Weeks |  | SOF + RBV 24 Weeks [Five subjects with missing cirrhosis status in the SOF + RBV 24-week group were excluded from this subgroup analysis.]
 | Treatment-Naïve (N=206) | Treatment-Experienced (N=71) | Treatment-Naïve (N=201) | Treatment-Experienced (N=69)
Without cirrhosis | 98% (160/163) | 94% (31/33) [One treatment-experienced subject without cirrhosis treated with EPCLUSA had genotype 1a HCV infection at failure, indicating HCV re-infection, and is therefore excluded from this analysis.] | 90% (141/156) | 71% (22/31)
With compensated cirrhosis | 93% (40/43) | 89% (33/37) | 73% (33/45) | 58% (22/38)
SOF = sofosbuvir; RBV = ribavirin.

14.3 Clinical Trial in Subjects Coinfected with HCV and HIV-1

ASTRAL-5 was an open-label trial that evaluated 12 weeks of treatment with EPCLUSA in subjects with genotype 1, 2, 3, 4, 5, or 6 HCV infection who were coinfected with HIV-1. Subjects were on a stable HIV-1 antiretroviral therapy that included emtricitabine/tenofovir disoproxil fumarate or abacavir/lamivudine administered with atazanavir/ritonavir, darunavir/ritonavir, lopinavir/ritonavir, rilpivirine, raltegravir or elvitegravir/cobicistat.

Of the 106 treated subjects, the median age was 57 years (range: 25 to 72); 86% of the subjects were male; 51% were White; 45% were Black; 22% had a baseline body mass index at least 30 kg/m^2; the proportions of patients with genotype 1, 2, 3, or 4 HCV infection were 74%, 10%, 11%, and 5%, respectively; no subjects with genotype 5 or 6 HCV were treated with EPCLUSA; 77% had non-CC IL28B alleles (CT or TT); 74% had baseline HCV RNA levels of at least 800,000 IU/mL; 18% had compensated cirrhosis; and 29% were treatment experienced. The overall mean CD4+ count was 598 cells/µL (range: 183−1513 cells/µL) and 57% of subjects had CD4+ counts > 500 cells/μL.

Table 17 presents the SVR12 for the ASTRAL-5 trial by HCV genotype.

Table 17 Study ASTRAL-5: Virologic Outcomes by HCV Genotype in Subjects Coinfected with HIV-1 without Cirrhosis or with Compensated Cirrhosis (12 Weeks After Treatment)
 | EPCLUSA 12 Weeks (N=106)
 | Total (all GTs) (N=106) | GT-1 |  |  | GT-2 (N=11) | GT-3 (N=12) | GT-4 (N=5)
 | Total (all GTs) (N=106) | GT-1a (N=66) | GT-1b (N=12) | Total (N=78) | GT-2 (N=11) | GT-3 (N=12) | GT-4 (N=5)
SVR12 | 95% (101/106) | 95% (63/66) | 92% (11/12) | 95% (74/78) | 100% (11/11) | 92% (11/12) | 100% (5/5)
Outcome for Subjects without SVR
On-Treatment Virologic Failure | 0/106 | 0/66 | 0/12 | 0/78 | 0/11 | 0/12 | 0/5
Relapse [The denominator for relapse is the number of subjects with HCV RNA <LLOQ at their last on-treatment assessment.] | 2% (2/103) | 3% (2/65) | 0/11 | 3% (2/76) | 0/11 | 0/11 | 0/5
Other [Other includes subjects who did not achieve SVR and did not meet virologic failure criteria.] | 3% (3/106) | 2% (1/66) | 8% (1/12) | 3% (2/78) | 0/11 | 8% (1/12) | (0/5)

No subject had HIV-1 rebound during treatment and CD4+ counts were stable during treatment.

14.4 Clinical Trials in Subjects with Decompensated Cirrhosis

ASTRAL-4 was a randomized, open-label trial in subjects with genotype 1, 2, 3, 4, 5, or 6 HCV infection and Child-Pugh B cirrhosis at screening. Subjects were randomized in a 1:1:1 ratio to treatment with EPCLUSA for 12 weeks (N=90), EPCLUSA with ribavirin for 12 weeks (N=87), or EPCLUSA for 24 weeks (N=90). Randomization was stratified by HCV genotype (1, 2, 3, 4, 5, 6, and indeterminate).

Demographics and baseline characteristics were balanced across the treatment groups. Of the 267 treated subjects, the median age was 59 years (range: 40 to 73); 70% of the subjects were male; 90% were White; 6% were Black; 42% had a baseline body mass index at least 30 kg/m^2. The proportions of subjects with genotype 1, 2, 3, 4, or 6 HCV were 78%, 4%, 15%, 3%, and less than 1% (1 subject), respectively. No subjects with genotype 5 HCV infection were enrolled. 76% had non-CC IL28B alleles (CT or TT); 56% had baseline HCV RNA levels at least 800,000 IU/mL; 55% were treatment-experienced; and 95% of subjects had Model for End Stage Liver Disease (MELD) score less than or equal to 15 at baseline. Although all subjects had Child-Pugh B cirrhosis at screening, 6% and 4% of subjects were assessed to have Child-Pugh A and Child-Pugh C cirrhosis, respectively, on the first day of treatment.

Treatment with EPCLUSA with ribavirin for 12 weeks resulted in numerically higher SVR12 rates than treatment with EPCLUSA for 12 weeks or 24 weeks. Because EPCLUSA with ribavirin for 12 weeks is the recommended dosage regimen, the results of the 12- and 24-week EPCLUSA treatment groups are not presented.

Table 18 presents the SVR12 for subjects treated with EPCLUSA with ribavirin for 12 weeks in the ASTRAL-4 trial by HCV genotype. No subjects with genotype 5 or 6 HCV were treated with EPCLUSA with ribavirin for 12 weeks.

Table 18 Study ASTRAL-4: Virologic Outcomes in Subjects with Decompensated Cirrhosis After 12 Weeks of Treatment by HCV Genotype
 | EPCLUSA + RBV 12 Weeks (N=87)
 | SVR12 | Virologic Failure (relapse and on-treatment failure)
Overall SVR12 [Includes subjects with baseline CPT C cirrhosis: all 4 subjects achieved SVR12.] | 94% (82/87) | 3% (3/87)
Genotype 1 | 96% (65/68) | 1% (1/68) [This subject with genotype 1a experienced relapse.]
Genotype 1a | 94% (51/54) | 2% (1/54)
Genotype 1b | 100% (14/14) | 0% (0/14)
Genotype 3 | 85% (11/13) | 15% (2/13) [One subject had on-treatment virologic failure; pharmacokinetic data from this subject was consistent with non- adherence.]
RBV = ribavirin.

All subjects with genotype 2 (N=4) and genotype 4 (N=2) HCV infection treated with EPCLUSA and ribavirin achieved SVR12.

14.5 Clinical Trial in Adult Liver Transplant Recipients without Cirrhosis and with Compensated Cirrhosis

Trial 2104 was an open-label clinical trial that evaluated 12 weeks of treatment with EPCLUSA in 79 HCV-infected treatment-naïve and previously treated adult subjects who had undergone liver transplantation. The proportions of subjects with genotype 1, 2, 3, or 4 HCV infection were 47%, 4%, 44%, and 5%, respectively. The median age was 62 years (range: 45 to 81); 81% were male; 82% were White; 3% were Black; and 15% were Asian; 28% had a baseline body mass index at least 30 kg/m^2. At baseline, 18% had compensated cirrhosis, and 60% were treatment experienced (subjects with prior exposure to any HCV NS5A inhibitor were excluded). Immunosuppressants allowed for coadministration were tacrolimus, mycophenolate mofetil, cyclosporine, and azathioprine. The overall SVR12 rate was 96% (76/79). Of the subjects completing 12 weeks of EPCLUSA, 2 subjects experienced virologic relapse.

14.6 Clinical Trial in Subjects with Severe Renal Impairment Requiring Dialysis

Trial 4062 was an open-label clinical trial that evaluated 12 weeks of treatment with EPCLUSA in 59 HCV-infected adults with ESRD requiring dialysis. The proportions of subjects with genotype 1, 2, 3, 4, 6 or indeterminate HCV infection were 42%,12%, 27%, 7%, 3%, and 8%, respectively. At baseline, 29% of subjects had cirrhosis, 22% were treatment-experienced (subjects with prior exposure to any HCV NS5A inhibitor were excluded), 92% were on hemodialysis, and 8% were on peritoneal dialysis; mean duration on dialysis was 7 years (range: 0 to 40 years). The overall SVR rate was 95% (56/59). Of the subjects completing 12 weeks of EPCLUSA, 1 subject experienced virologic relapse.

14.7 Clinical Trial in People who Inject Drugs (PWID), Including Those on Medication-Assisted Treatment (MAT) for Opioid Use Disorder

SIMPLIFY was an open-label Phase 2 clinical trial that evaluated 12 weeks of treatment with EPCLUSA in 103 HCV-infected PWID (defined as self-reported injection drug use within previous 6 months), including 58 subjects on MAT for opioid use disorder. The proportions of subjects with genotype 1, 2, 3, and 4 HCV infection were 35%, 5%, 58%, and 2%, respectively. The median age was 48 years (range: 24 to 67); 71% were male; 89% were White; and 2% were Black. At baseline, 74% and 26% of subjects reported injection drug use or daily injection drug use, respectively, in the past month; 56% had baseline HCV RNA levels at least 800,000 IU/mL; 10% had compensated cirrhosis; and all subjects were naïve to prior exposure with SOF or an HCV NS5A inhibitor. Subjects on MAT for opioid use disorder reported concomitant use of methadone (76%) and buprenorphine naloxone (17%) with EPCLUSA. The overall SVR rate was 94% (97/103). One subject completed EPCLUSA treatment and was re-infected with a phylogenetically different virus; the other 5 subjects who did not achieve SVR12 did not meet virologic failure criteria.

14.8 Clinical Trial in Pediatric Subjects

The efficacy of EPCLUSA once daily for 12 weeks was evaluated in an open-label trial (Study 1143) in 214 genotype 1, 2, 3, 4, or 6 HCV treatment-naïve (N=188) or treatment-experienced (N=26) pediatric subjects 3 years of age and older without cirrhosis or with compensated cirrhosis.

Subjects 12 Years to <18 Years of Age: EPCLUSA was evaluated in 102 subjects 12 years to <18 years of age with genotype 1, 2, 3, 4, or 6 HCV infection. Among these subjects, 80 (78%) were treatment-naïve and 22 (22%) were treatment-experienced. The median age was 15 years (range: 12 to 17); 51% of the subjects were female; 73% were White, 9% were Black, and 11% were Asian; 14% were Hispanic/Latino; mean body mass index was 23 kg/m^2 (range: 13 to 49 kg/m^2); mean weight was 61 kg (range: 22 to 147 kg); 58% had baseline HCV RNA levels greater than or equal to 800,000 IU/mL; the proportions of subjects with genotype 1, 2, 3, 4, or 6 HCV infection were 74%, 6%, 12%, 2%, and 6%, respectively; no subjects had known cirrhosis. The majority of subjects (89%) had been infected through vertical transmission.

The SVR rate was 93% (71/76) in subjects with genotype 1 HCV infection and 100% in subjects with genotype 2 (6/6), genotype 3 (12/12), genotype 4 (2/2), and genotype 6 (6/6) HCV infection. One subject discontinued treatment at Week 4 and subsequently relapsed; the other four subjects who did not achieve SVR12 did not meet virologic failure criteria (lost to follow-up).

Subjects 6 Years to <12 Years of Age: EPCLUSA was evaluated in 71 subjects 6 years to <12 years of age with genotype 1, 2, 3, or 4 HCV infection. Among these subjects, 67 (94%) were treatment-naïve and 4 (6%) were treatment-experienced. The median age was 8 years (range: 6 to 11); 54% of the subjects were female; 90% were White, 6% were Black, and 1% were Asian; 10% were Hispanic/Latino; mean body mass index was 17 kg/m^2 (range: 13 to 31 kg/m^2); mean weight was 30 kg (range: 18 to 78 kg); 48% had baseline HCV RNA levels greater than or equal to 800,000 IU per mL; the proportions of subjects with genotype 1, 2, 3, or 4 HCV infection were 76%, 3%, 15%, and 6%, respectively; no subjects had known cirrhosis. The majority of subjects (94%) had been infected through vertical transmission.

The SVR rate was 93% (50/54) in subjects with genotype 1 HCV infection, 91% (10/11) in subjects with genotype 3 HCV infection, and 100% in subjects with genotype 2 (2/2) and genotype 4 (4/4) HCV infection. One subject had on-treatment virologic failure; the other four subjects who did not achieve SVR12 did not meet virologic failure criteria (lost to follow-up).

Subjects 3 Years to <6 Years of Age: EPCLUSA was evaluated in 41 treatment-naïve subjects 3 years to <6 years of age with genotype 1, 2, 3, or 4 HCV infection. The median age was 4 years (range: 3 to 5); 59% of the subjects were female; 78% were White, 7% were Black; 10% were Hispanic/Latino; mean body mass index was 17.0 kg/m^2 (range: 13.9 to 22.0 kg/m^2); mean weight was 19 kg (range: 13 to 35 kg); 49% had baseline HCV RNA levels greater than or equal to 800,000 IU per mL; the proportions of subjects with genotype 1, 2, 3, or 4 HCV infection were 78%, 15%, 5%, and 2%, respectively; no subjects had known cirrhosis. The majority of subjects (98%) had been infected through vertical transmission.

The SVR12 rate among all subjects was 83% (34/41); with 88% (28/32) in subjects with genotype 1 HCV infection, 50% (3/6) in subjects with genotype 2 HCV infection, and 100% in subjects with genotype 3 (2/2) and genotype 4 (1/1) HCV infection. None of the 34 subjects who completed the treatment had virologic failure. Of the remaining seven subjects who did not achieve SVR12, five discontinued treatment on Day 1, one on Day 7, and one on Day 20 [see Adverse Reactions (6.1)].

16 HOW SUPPLIED/STORAGE AND HANDLING

Tablets

EPCLUSA tablets, 400 mg/100 mg, are pink, diamond-shaped, film-coated, debossed with "GSI" on one side and "7916" on the other. Each bottle contains 28 tablets (NDC 61958-2201-1), polyester coil, and is closed with a child-resistant closure.

EPCLUSA tablets, 200 mg/50 mg, are pink, oval-shaped, film-coated, debossed with "GSI" on one side and "S/V" on the other. Each bottle contains 28 tablets (NDC 61958-2203-1), polyester coil, and is closed with a child-resistant closure.

STORAGE AND HANDLING

- Store below 30 °C (86 ºF).
- Dispense only in original container.

Oral Pellets

EPCLUSA oral pellets, 200 mg/50 mg, are white to off-white, film-coated pellets supplied as unit-dose packets in cartons. Each carton contains 28 packets (NDC 61958-2204-1).

EPCLUSA oral pellets, 150 mg/37.5 mg, are white to off-white, film-coated pellets supplied as unit-dose packets in cartons. Each carton contains 28 packets (NDC 61958-2205-1).

STORAGE AND HANDLING

- Store below 30 °C (86 ºF).
- Do not use if carton tamper-evident seal or packet has been opened or damaged.

17 PATIENT COUNSELING INFORMATION

Advise the patient to read the FDA-approved patient labeling (Patient Information and Instructions for Use).

Risk of Hepatitis B Virus Reactivation in Patients Coinfected with HCV and HBV

Inform patients that HBV reactivation can occur in patients coinfected with HBV during or after treatment of HCV infection. Advise patients to tell their healthcare provider if they have a history of HBV infection [see Warnings and Precautions (5.1)].

Serious Symptomatic Bradycardia When Coadministered with Amiodarone

Advise patients to seek medical evaluation immediately for symptoms of bradycardia such as near-fainting or fainting, dizziness or lightheadedness, malaise, weakness, excessive tiredness, shortness of breath, chest pain, confusion, or memory problems [see Warnings and Precautions (5.2), Adverse Reactions (6.2), and Drug Interactions (7.3)].

Drug Interactions

Inform patients that EPCLUSA may interact with other drugs. Advise patients to report to their healthcare provider the use of any other prescription or nonprescription medication or herbal products including St. John's wort [see Warnings and Precautions (5.2, 5.3) and Drug Interactions (7)].

Administration

Advise patients to take EPCLUSA once daily on a regular dosing schedule with or without food. Inform patients that it is important not to miss or skip doses and to take EPCLUSA for the duration that is recommended by the physician.

For EPCLUSA oral pellets, advise patients or caregivers to read and follow the Instructions for Use for preparing the correct dose [see Dosage and Administration (2.4, 2.5)].

Pregnancy

Advise patients to avoid pregnancy during combination treatment with EPCLUSA and ribavirin and for 6 months after completion of treatment. Inform patients to notify their healthcare provider immediately in the event of a pregnancy [see Use in Specific Populations (8.1)].

Manufactured and distributed by:
Gilead Sciences, Inc.
Foster City, CA 94404

EPCLUSA, ATRIPLA, COMPLERA, GENVOYA, HARVONI, and STRIBILD are trademarks of Gilead Sciences, Inc., or its related companies. All other trademarks referenced herein are the property of their respective owners.

© 2022 Gilead Sciences, Inc. All rights reserved.
208341-GS-010

PATIENT INFORMATION

EPCLUSA® (ep-KLOO-suh)
(sofosbuvir and velpatasvir)
tablets

EPCLUSA® (ep-KLOO-suh)
(sofosbuvir and velpatasvir)
oral pellets

Important: If you take EPCLUSA with ribavirin, you should also read the Medication Guide for ribavirin.

What is the most important information I should know about EPCLUSA?
EPCLUSA can cause serious side effects, including:
Hepatitis B virus reactivation: Before starting treatment with EPCLUSA, your healthcare provider will do blood tests to check for hepatitis B virus infection. If you have ever had hepatitis B virus infection, the hepatitis B virus could become active again during or after treatment of hepatitis C virus with EPCLUSA. Hepatitis B virus becoming active again (called reactivation) may cause serious liver problems including liver failure and death. Your healthcare provider will monitor you if you are at risk for hepatitis B virus reactivation during treatment and after you stop taking EPCLUSA.
For more information about side effects, see the section "What are the possible side effects of EPCLUSA?"

What is EPCLUSA?
EPCLUSA is a prescription medicine used to treat adults and children 3 years of age and older with chronic (lasting a long time) hepatitis C virus (HCV) genotype 1, 2, 3, 4, 5, or 6 infection:

- without cirrhosis or with compensated cirrhosis.
- with advanced cirrhosis (decompensated) in combination with ribavirin.

EPCLUSA contains the two medicines: sofosbuvir and velpatasvir.
It is not known if EPCLUSA is safe and effective in children under 3 years of age.

Before taking EPCLUSA, tell your healthcare provider about all of your medical conditions, including if you:

- have ever had hepatitis B virus infection
- have liver problems other than hepatitis C infection
- have had a liver transplant
- have kidney problems or you are on dialysis
- have HIV-1 infection
- are pregnant or plan to become pregnant. It is not known if EPCLUSA will harm your unborn baby.
  - Females who take EPCLUSA in combination with ribavirin should avoid becoming pregnant during treatment and for 6 months after stopping treatment. Call your healthcare provider right away if you think you may be pregnant or become pregnant during treatment with EPCLUSA in combination with ribavirin.
  - Males and females who take EPCLUSA in combination with ribavirin should also read the ribavirin Medication Guide for important pregnancy, contraception, and infertility information.
- are breastfeeding or plan to breastfeed. It is not known if EPCLUSA passes into your breast milk.
  - Talk to your healthcare provider about the best way to feed your baby during treatment with EPCLUSA.

Tell your healthcare provider about all of the medicines you take, including prescription and over-the-counter medicines, vitamins, and herbal supplements. EPCLUSA and other medicines may affect each other. This can cause you to have too much or not enough EPCLUSA or other medicines in your body. This may affect the way EPCLUSA or your other medicines work or may cause side effects.
Keep a list of your medicines to show your healthcare provider and pharmacist.

- You can ask your healthcare provider or pharmacist for a list of medicines that interact with EPCLUSA.
- Do not start taking a new medicine without telling your healthcare provider. Your healthcare provider can tell you if it is safe to take EPCLUSA with other medicines.

How should I take EPCLUSA?

- Take EPCLUSA exactly as your healthcare provider tells you to take it. Do not change your dose unless your healthcare provider tells you to.
- Do not stop taking EPCLUSA without first talking with your healthcare provider.
- Take EPCLUSA oral pellets or tablets by mouth, with or without food.
- For adults the usual dose of EPCLUSA is one 400/100 mg tablet each day.
- For children 3 years of age and older your healthcare provider will prescribe the right dose of EPCLUSA oral pellets or tablets based on your child's body weight.
  - Tell your healthcare provider if your child has problems with swallowing tablets.
  - If your healthcare provider prescribes EPCLUSA oral pellets for your child, see "How should I give EPCLUSA oral pellets to my child?"
- Do not miss a dose of EPCLUSA. Missing a dose lowers the amount of medicine in your blood. Refill your EPCLUSA prescription before you run out of medicine.
- If you take too much EPCLUSA, call your healthcare provider or go to the nearest hospital emergency room right away.

How should I give EPCLUSA oral pellets to my child?

See the detailed Instructions for Use for information about how to give or take a dose of EPCLUSA oral pellets.

- Administer EPCLUSA oral pellets exactly as instructed by your healthcare provider.
- EPCLUSA oral pellets can be taken with food or directly in the mouth.
- For children younger than 6 years, take EPCLUSA oral pellets with food.
- EPCLUSA oral pellets should be swallowed whole. Do not chew EPCLUSA oral pellets to avoid a bitter after taste.
- Do not open the EPCLUSA oral pellets packet until ready to use.

What are the possible side effects of EPCLUSA?
EPCLUSA can cause serious side effects, including:

- Hepatitis B virus reactivation. See "What is the most important information I should know about EPCLUSA?"
- Slow heart rate (bradycardia). EPCLUSA treatment may result in slowing of the heart rate along with other symptoms when taken with amiodarone (Cordarone®, Nexterone®, Pacerone®), a medicine used to treat certain heart problems. In some cases bradycardia has led to death or the need for a heart pacemaker when amiodarone is taken with medicines similar to EPCLUSA that contain sofosbuvir. Get medical help right away if you take amiodarone with EPCLUSA and get any of the following symptoms:

- fainting or near-fainting
- dizziness or lightheadedness
- not feeling well
- weakness
- extreme tiredness

- shortness of breath
- chest pains
- confusion
- memory problems

- The most common side effects of EPCLUSA in adults and children 6 years of age and older include headache and tiredness.
- The most common side effects of EPCLUSA when used with ribavirin in adults with decompensated cirrhosis are tiredness, low red blood cells, nausea, headache, trouble sleeping, and diarrhea.
- The most common side effects of EPCLUSA in children younger than 6 years of age are vomiting and problems with spitting up the medicine.

These are not all the possible side effects of EPCLUSA.
Call your doctor for medical advice about side effects. You may report side effects to FDA at 1-800-FDA-1088.

How should I store EPCLUSA?

- Store EPCLUSA tablets or oral pellets below 86°F (30°C).
- Keep EPCLUSA tablets in the original container.
- Do not use EPCLUSA oral pellets if the carton tamper-evident seal or the packet has been opened or damaged.

Keep EPCLUSA and all medicines out of the reach of children.

General information about the safe and effective use of EPCLUSA
Medicines are sometimes prescribed for purposes other than those listed in a Patient Information leaflet. Do not use EPCLUSA for a condition for which it was not prescribed. Do not give EPCLUSA to other people, even if they have the same symptoms you have. It may harm them.
You can ask your healthcare provider or pharmacist for information about EPCLUSA that is written for health professionals.

What are the ingredients in EPCLUSA?
Active ingredients: sofosbuvir and velpatasvir
Inactive ingredients, Tablets: copovidone, croscarmellose sodium, magnesium stearate, and microcrystalline cellulose.
The tablet film-coat contains: iron oxide red, polyethylene glycol, polyvinyl alcohol, talc, and titanium dioxide.
Inactive ingredients, Oral Pellets: colloidal silicon dioxide, copovidone, croscarmellose sodium, lactose monohydrate, magnesium stearate, and microcrystalline cellulose.
The oral pellets film-coat contains: amino methacrylate copolymer, colloidal silicon dioxide, hypromellose, L‑tartaric acid, polyethylene glycol, stearic acid, talc, and titanium dioxide.
Manufactured and distributed by:
Gilead Sciences, Inc., Foster City, CA 94404
EPCLUSA is a trademark of Gilead Sciences, Inc., or its related companies. All other trademarks referenced herein are the property of their respective owners.
©2022 Gilead Sciences, Inc. All rights reserved.
For more information, call 1-800-445-3235 or go to www.epclusa.com.
208341-GS-010

This Patient Information has been approved by the U.S. Food and Drug Administration.

Revised: 06/2021

INSTRUCTIONS FOR USE EPCLUSA® (ep-KLOO-suh) (sofosbuvir and velpatasvir) pellets, for oral use

Read the Patient Information that comes with EPCLUSA oral pellets for important information about EPCLUSA.

This Instructions for Use contains information on how to take EPCLUSA oral pellets. Be sure you understand and follow the instructions. If you have any questions, ask your healthcare provider or pharmacist.

Important Information You Need to Know Before Taking EPCLUSA oral pellets

- For oral use only (take by mouth with or without food).
- Pellets should be swallowed whole. Do not chew pellets.
- Do not open the EPCLUSA oral pellet packet(s) until ready to use.
- For children younger than 6 years, take EPCLUSA oral pellets with food.
- EPCLUSA oral pellets are white to off-white pellets supplied as single-use packets in cartons. Each carton contains 28 packets.
- Do not use EPCLUSA oral pellets if the carton tamper-evident seal or the packet has been opened or damaged.

Gather Supplies:

Before you prepare a dose of EPCLUSA oral pellets, gather the following supplies:

- Daily EPCLUSA oral pellet packet(s), as prescribed by your healthcare provider
- Scissors (optional)

If taking EPCLUSA oral pellets with food, gather the following additional supplies:

- One or more spoonfuls of non-acidic soft food such as pudding, chocolate syrup, or ice cream
- Bowl
- Spoon

Prepare and Administer a Dose:

Step 1: If taking EPCLUSA oral pellets with food, add one or more spoonfuls of non-acidic soft food to the bowl first.

Step 2: Hold the EPCLUSA oral pellets packet with the cut line on top (see Figure A).

Step 3: Shake the packet gently to settle the pellets to the bottom of the packet (see Figure B).

Figure A

Figure B

Step 4: Cut the packet along the cut line with scissors (see Figure C), or fold the packet back at the tear line (see Figure D) and tear open (see Figure E).

Figure C

Figure D

Figure E

Step 5:

- If taking EPCLUSA oral pellets with food, carefully pour the entire contents of the prescribed number of EPCLUSA oral pellet packet(s) onto the food in the bowl and gently mix with a spoon (see Figure F). Take the EPCLUSA oral pellets and food mixture within 15 minutes without chewing to avoid a bitter taste.
- If taking EPCLUSA oral pellets by mouth, pour the entire contents of the prescribed number of EPCLUSA oral pellet packet(s) directly in the mouth and swallow without chewing to avoid a bitter taste (see Figure G). Water may be taken after swallowing the pellets, if needed.

Figure F

Figure G

Step 6: Make sure all of the EPCLUSA oral pellets are taken. Make sure that no EPCLUSA oral pellets remain in the packet(s) or in the food.

Storing EPCLUSA oral pellets

- Store EPCLUSA pellets below 86°F (30°C).
- Keep EPCLUSA oral pellets and all medicines out of the reach of children.

Disposing of EPCLUSA oral pellets

- Throw away (dispose of) any unused portion. Do not store and reuse any leftover EPCLUSA oral pellets or EPCLUSA mixture (oral pellets mixed with food).

For more information, call 1-800-445-3235 or go to www.EPCLUSA.com.

Manufactured for and distributed by: Gilead Sciences, Inc., Foster City, CA 94404
EPCLUSA is a trademark of Gilead Sciences, Inc., or its related companies.

© 2022 Gilead Sciences, Inc. All rights reserved.
208341-GS-010

This Instructions for Use has been approved by the U.S. Food and Drug Administration.
Issued: June 2021

PRINCIPAL DISPLAY PANEL - 400 mg/100 mg Tablet Bottle Label

NDC 61958-2201-1
28 tablets

Epclusa®
(sofosbuvir and
velpatasvir) tablets
400 mg / 100 mg

Take 1 tablet once daily

Note to pharmacist:
Do not cover ALERT box with pharmacy label.

ALERT: Find out about medicines that
should NOT be taken with Epclusa

PRINCIPAL DISPLAY PANEL - 200 mg/50 mg Tablet Bottle Label

NDC 61958-2203-1
28 tablets

Epclusa®
(sofosbuvir and velpatasvir)
tablets

200 mg/50 mg

Note to pharmacist:
Do not cover ALERT box with pharmacy label.

ALERT: Find out about medicines that
should NOT be taken with Epclusa

PRINCIPAL DISPLAY PANEL - 200 mg/50 mg Packet Carton

NDC 61958-2204-1
28 packets

Rx only

Epclusa®
(sofosbuvir and velpatasvir) oral pellets

200 mg/50 mg per packet

Pellets should be swallowed whole. Do not chew pellets.

Note to pharmacist: Do not cover ALERT box with pharmacy label.

ALERT: Find out about medicines that should NOT be taken with Epclusa

GILEAD

PRINCIPAL DISPLAY PANEL - 150 mg/37.5 mg Packet Carton

NDC 61958-2205-1
28 packets

Rx only

Epclusa®
(sofosbuvir and velpatasvir) oral pellets

150 mg/37.5 mg per packet

Pellets should be swallowed whole. Do not chew pellets.

Note to pharmacist: Do not cover ALERT box with pharmacy label.

ALERT: Find out about medicines that should NOT be taken with Epclusa

GILEAD